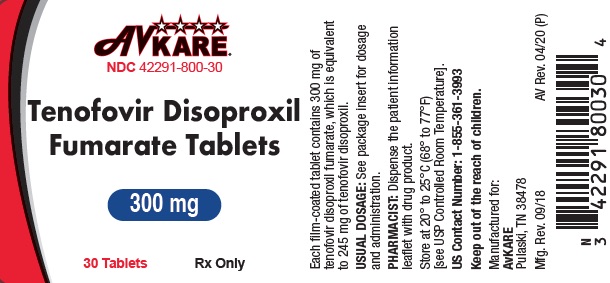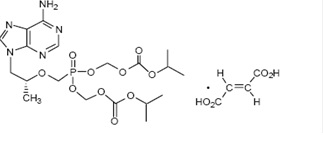 DRUG LABEL: Tenofovir Disoproxil Fumarate
NDC: 42291-800 | Form: TABLET, FILM COATED
Manufacturer: AvKARE
Category: prescription | Type: HUMAN PRESCRIPTION DRUG LABEL
Date: 20260115

ACTIVE INGREDIENTS: TENOFOVIR DISOPROXIL FUMARATE 300 mg/1 1
INACTIVE INGREDIENTS: CROSCARMELLOSE SODIUM; LACTOSE MONOHYDRATE; MAGNESIUM STEARATE; CELLULOSE, MICROCRYSTALLINE; STARCH, CORN; HYPROMELLOSES; TITANIUM DIOXIDE; TRIACETIN

HIGHLIGHTS OF PRESCRIBING INFORMATION

TENOFOVIR DISOPROXIL FUMARATE tablets, for oral use
Rx only
These highlights do not include all the information needed to use TENOFOVIR DISOPROXIL FUMARATE TABLETS safely and effectively. See full prescribing information for TENOFOVIR DISOPROXIL FUMARATE TABLETS.
TENOFOVIR DISOPROXIL FUMARATE tablets, for oral use
Initial U.S. Approval: 2001

RECENT MAJOR CHANGES

Indications and Usage (1.1) 07/2018
Warnings and Precautions, Coadministration with
Other Products (5.4) 07/2018

BOXED WARNING

WARNING: POSTTREATMENT EXACERBATION OF HEPATITIS
See full prescribing information for complete boxed warning.
Severe acute exacerbations of hepatitis have been reported in HBV-infected patients who have discontinued anti-hepatitis B therapy, including tenofovir disoproxil fumarate tablets. Hepatic function should be monitored closely in these patients. If appropriate, resumption of anti-hepatitis B therapy may be warranted. (5.1)

1 INDICATIONS & USAGE

Tenofovir disoproxil fumarate tablets are a nucleotide analog HIV-1 reverse transcriptase inhibitor and an HBV reverse transcriptase inhibitor.

- Tenofovir disoproxil fumarate tablets are indicated in combination with other antiretroviral agents for the treatment of HIV-1 infection in adults and pediatric patients 2 years of age and older. (1)
- Tenofovir disoproxil fumarate tablets are indicated for the treatment of chronic hepatitis B in adults and pediatric patients 12 years of age and older. (1)

2 DOSAGE & ADMINISTRATION

• Recommended dose for the treatment of HIV-1 or chronic hepatitis B in adults and pediatric patients 12 years of age and older (35 kg or more): 300 mg once daily taken orally without regard to food. (2.1)
• Recommended dose for the treatment of HIV-1 in pediatric patients (2 to less than 12 years of age):
o Tablets: For pediatric patients weighing greater than or equal to 17 kg who can swallow an intact tablet, one tenofovir disoproxil fumarate tablet (300 mg based on body weight) once daily taken orally without regard to food. (2.2)
• Dose recommended in renal impairment in adults:
o Creatinine clearance 30 to 49 mL/min: 300 mg every 48 hours. (2.3)
o Creatinine clearance 10 to 29 mL/min: 300 mg every 72 to 96 hours. (2.3)
o Hemodialysis: 300 mg every 7 days or after approximately 12 hours of dialysis. (2.3)

3 DOSAGE FORMS & STRENGTHS

• Tablets: 300 mg (3)

4 CONTRAINDICATIONS

None. (4)

5 WARNINGS AND PRECAUTIONS

• New onset or worsening renal impairment: Can include acute renal failure and Fanconi syndrome. Assess estimated creatinine clearance before initiating treatment with tenofovir disoproxil fumarate tablets. In patients at risk for renal dysfunction, assess estimated creatinine clearance, serum phosphorus, urine glucose, and urine protein before initiating treatment with tenofovir disoproxil fumarate tablets and periodically during treatment. Avoid administering tenofovir disoproxil fumarate tablets with concurrentor recent use of nephrotoxic drugs. (5.2)
• Lactic acidosis/severe hepatomegaly with steatosis: Discontinue treatment in patients who develop symptoms or laboratory findings suggestive of lactic acidosis or pronounced hepatotoxicity. (5.3)
• Coadministration with other products: Do not use with other tenofovir-containing products (e.g., ATRIPLA, BIKTARVY, COMPLERA, DESCOVY, GENVOYA, ODEFSEY, STRIBILD, TRUVADA, or VEMLIDY). Do not administer in combination with HEPSERA. (5.4)
• HIV testing: HIV antibody testing should be offered to all HBV-infected patients before initiating therapy with tenofovir disoproxil fumarate tablets. Tenofovir disoproxil fumarate tablets should only be used as part of an appropriate antiretroviral combination regimen in HIV-infected patients with or without HBV coinfection. (5.5)
• Decreases in bone mineral density (BMD): Consider assessment of BMD in patients with a history of pathologic fracture or other risk factors for osteoporosis or bone loss. (5.6)
• Immune reconstitution syndrome: Observed in HIV-infected patients. May necessitate further evaluation and treatment. (5.7)
• Triple nucleoside-only regimens: Early virologic failure has been reported in HIV-infected patients. Monitor carefully and consider treatment modification. (5.8)

6 ADVERSE REACTIONS

• In HIV-infected adult subjects: Most common adverse reactions (incidence greater than or equal to 10%, Grades 2 to 4) are rash, diarrhea, headache, pain, depression, asthenia, and nausea. (6.1)
• In HBV-infected subjects with compensated liver disease: Most common adverse reaction (all grades) was nausea (9%). (6.1)
• In pediatric subjects: Adverse reactions in pediatric subjects were consistent with those observed in adults. (6.1)
• In HBV-infected subjects with decompensated liver disease: Most common adverse reactions (incidence greater than or equal to 10%, all grades) were abdominal pain, nausea, insomnia, pruritus, vomiting, dizziness, and pyrexia. (6.1)
To report SUSPECTED ADVERSE REACTIONS, contact AvKARE at 1-855-361-3993 or FDA at 1-800-FDA-1088 or www.fda.gov/medwatch

7 DRUG INTERACTIONS

• Tenofovir disoproxil fumarate increases didanosine concentrations. Dose reduction and close monitoring for didanosine toxicity are warranted. (7.2)
• Coadministration decreases atazanavir concentrations. When coadministered with tenofovir disoproxil fumarate, use atazanavir given with ritonavir. (7.2)
• Coadministration of tenofovir disoproxil fumarate with certain HIV-1 protease inhibitors or certain drugs to treat HCV increases tenofovir concentrations. Monitor for evidence of tenofovir toxicity. (7.2)
• Consult Full Prescribing Information prior to and during treatment for important drug interactions. (7.2)

8 USE IN SPECIFIC POPULATIONS

Nursing mothers: Women infected with HIV should be instructed not to breastfeed. (8.3)

FULL PRESCRIBING INFORMATION

BOXED WARNING

WARNING: POSTTREATMENT EXACERBATION OF HEPATITIS
Severe acute exacerbations of hepatitis have been reported in HBV-infected patients who have discontinued anti-hepatitis B therapy, including tenofovir disoproxil fumarate tablets. Hepatic function should be monitored closely with both clinical and laboratory follow-up for at least several months in patients who discontinue anti-hepatitis B therapy, including tenofovir disoproxil fumarate tablets. If appropriate, resumption of anti-hepatitis B therapy may be warranted [See Warnings and Precautions (5.1)].

1 INDICATIONS & USAGE

1.1 HIV-1 Infection

Tenofovir disoproxil fumarate tablets are indicated in combination with other antiretroviral agents for the treatment of HIV-1 infection in adults and pediatric patients 2 years of age and older.
The following points should be considered when initiating therapy with tenofovir disoproxil fumarate tablets for the treatment of HIV-1 infection:

- Tenofovir disoproxil fumarate tablets should not be used in combination with ATRIPLA®, BIKTARVY®, COMPLERA®, DESCOVY®, GENVOYA®, ODEFSEY®, STRIBILD®, TRUVADA®, or VEMLIDY® [See Warnings and Precautions (5.4)].

1.2 Chronic Hepatitis B

Tenofovir disoproxil fumarate tablets are indicated for the treatment of chronic hepatitis B in adults and pediatric patients 12 years of age and older.
The following points should be considered when initiating therapy with tenofovir disoproxil fumarate tablets for the treatment of chronic hepatitis B infection:

- The indication in adults is based on safety and efficacy data from treatment of subjects who were nucleoside-treatment-naïve and subjects who were treatment-experienced with documented resistance to lamivudine. Subjects were adults with HBeAg-positive and HBeAg-negative chronic hepatitis B with compensated liver disease [See Clinical Studies (14.2)].
- Tenofovir disoproxil fumarate tablets were evaluated in a limited number of subjects with chronic hepatitis B and decompensated liver disease [See Adverse Reactions (6.1),Clinical Studies (14.2)].
- The numbers of subjects in clinical trials who had adefovir resistance-associated substitutions at baseline were too small to reach conclusions of efficacy [See Microbiology (12.4),Clinical Studies (14.2)].

2 DOSAGE & ADMINISTRATION

2.1 Recommended Dose in Adults and Pediatric Patients 12 Years of Age and Older (35 kg or more)

For the treatment of HIV-1 or chronic hepatitis B: The dose is one 300 mg tenofovir disoproxil fumarate tablet once daily taken orally, without regard to food.
In the treatment of chronic hepatitis B, the optimal duration of treatment is unknown. Safety and efficacy in pediatric patients with chronic hepatitis B weighing less than 35 kg have not been established.

2.2 Recommended Dose in Pediatric Patients 2 Years to Less than 12 Years of Age

HIV-1 Infection
For the treatment of HIV-1 in pediatric patients 2 years of age and older, the recommended oral dose of tenofovir disoproxil fumarate tablet is 8 mg of tenofovir disoproxil fumarate (tenofovir DF) per kilogram of body weight (up to a maximum of 300 mg) once daily administered as tablets.
Tenofovir disoproxil fumarate is available as tablets in 300 mg strength for pediatric patients who weigh greater than or equal to 17 kg and who are able to reliably swallow intact tablets. The dose is one tablet once daily taken orally, without regard to food.
Table 2 contain dosing recommendations for tenofovir disoproxil fumarate tablets based on body weight. Weight should be monitored periodically and the tenofovir disoproxil fumarate tablets dose adjusted accordingly.
Table 2 Dosing Recommendations for Pediatric Patients 2 Years of Age and Older and Weighing At Least 17 kg Using Tenofovir Disoproxil Fumarate Tablets

Body Weight Kilogram (kg) | Tablets Once Daily
17 to less than 22 | 150 mg
22 to less than 28 | 200 mg
28 to less than 35 | 250 mg
35 or greater | 300 mg

Chronic Hepatitis B
Safety and efficacy of tenofovir disoproxil fumarate tablets in patients younger than 12 years of age have not been established.

2.3 Dose Adjustment for Renal Impairment in Adults

Significantly increased drug exposures occurred when tenofovir disoproxil fumarate tablets were administered to subjects with moderate to severe renal impairment [See Clinical Pharmacology (12.3)]. Therefore, the dosing interval of tenofovir disoproxil fumarate tablets 300 mg should be adjusted in patients with baseline creatinine clearance below 50 mL/min using the recommendations in Table 3. These dosing interval recommendations are based on modeling of single-dose pharmacokinetic data in non-HIV and non-HBV infected subjects with varying degrees of renal impairment, including end-stage renal disease requiring hemodialysis. The safety and effectiveness of these dosing interval adjustment recommendations have not been clinically evaluated in patients with moderate or severe renal impairment; therefore, clinical response to treatment and renal function should be closely monitored in these patients [See Warnings and Precautions (5.2)].

No dose adjustment of tenofovir disoproxil fumarate tablets 300 mg is necessary for patients with mild renal impairment (creatinine clearance 50 to 80 mL/min). Routine monitoring of estimated creatinine clearance, serum phosphorus, urine glucose, and urine protein should be performed in patients with mild renal impairment [See Warnings and Precautions (5.2)].

Table 3 Dosage Adjustment for Patients with Altered Creatinine Clearance

 | Creatinine Clearance (mL/min)a |  |  | Hemodialysis Patients
 | 50 or greater | 30- 49 | 10- 29 | Hemodialysis Patients
Recommended 300 mg Dosing Interval | Every 24 hours | Every 48 hours | Every 72 to 96 hours | Every 7 days or after a tot al of approximately 12 hours of dialysis

a. Calculated using ideal (lean) body weight.
b. Generally once weekly assuming three hemodialysis sessions a week of approximately 4 hours duration. Tenofovir disoproxil fumarate tablets should be administered following completion of dialysis.

3 DOSAGE FORMS & STRENGTHS

Tenofovir disoproxil fumarate is available as tablets.
Tenofovir disoproxil fumarate tablets contain 300 mg of tenofovir disoproxil fumarate, which is equivalent to 245 mg of tenofovir disoproxil. The tablets are white, almond shaped, film coated debossed with ‘H’ on one side and ‘123’ on other side.

4 CONTRAINDICATIONS

None.

5 WARNINGS AND PRECAUTIONS

5.1 Exacerbation of Hepatitis after Discontinuation of Treatment

Discontinuation of anti-HBV therapy, including tenofovir disoproxil fumarate tablets, may be associated with severe acute exacerbations of hepatitis. Patients infected with HBV who discontinue tenofovir disoproxil fumarate tablets should be closely monitored with both clinical and laboratory follow-up for at least several months after stopping treatment. If appropriate, resumption of anti-hepatitis B therapy may be warranted.

5.2 New Onset or Worsening Renal Impairment

Tenofovir is principally eliminated by the kidney. Renal impairment, including cases of acute renal failure and Fanconi syndrome (renal tubular injury with severe hypophosphatemia), has been reported with the use of tenofovir disoproxil fumarate tablets [See Adverse Reactions (6.2)].
It is recommended that estimated creatinine clearance be assessed in all patients prior to initiating therapy and as clinically appropriate during therapy with tenofovir disoproxil fumarate tablets. In patients at risk of renal dysfunction, including patients who have previously experienced renal events while receiving HEPSERA®, it is recommended that estimated creatinine clearance, serum phosphorus, urine glucose, and urine protein be assessed prior to initiation of tenofovir disoproxil fumarate tablets, and periodically during tenofovir disoproxil fumarate tablets therapy.
Dosing interval adjustment of tenofovir disoproxil fumarate tablets and close monitoring of renal function are recommended in all patients with creatinine clearance below 50 mL/min [See Dosage and Administration (2.3)].No safety or efficacy data are available in patients with renal impairment who received tenofovir disoproxil fumarate tablets using these dosing guidelines, so the potential benefit of tenofovir disoproxil fumarate tablets therapy should be assessed against the potential risk of renal toxicity.
Tenofovir disoproxil fumarate tablets should be avoided with concurrent or recent use of a nephrotoxic agent (e.g., high-dose or multiple non-steroidal anti-inflammatory drugs (NSAIDs)) [See Drug Interactions (7.1)].Cases of acute renal failure after initiation of high dose or multiple NSAIDs have been reported in HIV-infected patients with risk factors for renal dysfunction who appeared stable on tenofovir DF. Some patients required hospitalization and renal replacement therapy. Alternatives to NSAIDs should be considered, if needed, in patients at risk for renal dysfunction.
Persistent or worsening bone pain, pain in extremities, fractures and/or muscular pain or weakness may be manifestations of proximal renal tubulopathy and should prompt an evaluation of renal function in at-risk patients.

5.3 Lactic Acidosis/Severe Hepatomegaly with Steatosis

Lactic acidosis and severe hepatomegaly with steatosis, including fatal cases, have been reported with the use of nucleoside analogs, including tenofovir DF, alone or in combination with other antiretrovirals. Treatment with tenofovir disoproxil fumarate tablets should be suspended in any patient who develops clinical or laboratory findings suggestive of lactic acidosis or pronounced hepatotoxicity (which may include hepatomegaly and steatosis even in the absence of marked transaminase elevations).

5.4 Coadministration with Other Products

Tenofovir disoproxil fumarate tablets should not be used in combination with other drugs containing tenofovir DF or tenofovir alafenamide, including ATRIPLA, BIKTARVY, COMPLERA, DESCOVY, GENVOYA, ODEFSEY, STRIBILD, TRUVADA, or VEMLIDY. Tenofovir disoproxil fumarate tablets should not be administered in combination with HEPSERA (adefovir dipivoxil) [See Drug Interactions (7.2)].

5.5 Patients Coinfected with HIV-1 and HBV

Due to the risk of development of HIV-1 resistance, tenofovir disoproxil fumarate tablets should only be used in HIV-1 and HBV coinfected patients as part of an appropriate antiretroviral combination regimen.
HIV-1 antibody testing should be offered to all HBV-infected patients before initiating therapy with tenofovir disoproxil fumarate tablets. It is also recommended that all patients with HIV-1 be tested for the presence of chronic hepatitis B before initiating treatment with tenofovir disoproxil fumarate tablets.

5.6 Bone Effects

Bone Mineral Density:
In clinical trials in HIV-1 infected adults, tenofovir disoproxil fumarate tablets were associated with slightly greater decreases in bone mineral density (BMD) and increases in biochemical markers of bone metabolism, suggesting increased bone turnover relative to comparators. Serum parathyroid hormone levels and 1,25 Vitamin D levels were also higher in subjects receiving tenofovir disoproxil fumarate tablets [See Adverse Reactions (6.1)].
Clinical trials evaluating tenofovir disoproxil fumarate tablets in pediatric and adolescent subjects were conducted. Under normal circumstances, BMD increases rapidly in pediatric patients. In HIV-1 infected subjects aged 2 years to less than 18 years, bone effects were similar to those observed in adult subjects and suggest increased bone turnover. Total body BMD gain was less in the tenofovir disoproxil fumarate-treated HIV-1 infected pediatric subjects as compared to the control groups. Similar trends were observed in chronic hepatitis B infected adolescent subjects aged 12 years to less than 18 years. In all pediatric trials, skeletal growth (height) appeared to be unaffected [See Adverse Reactions (6.1)].
The effects of tenofovir disoproxil fumarate-associated changes in BMD and biochemical markers on long-term bone health and future fracture risk are unknown. Assessment of BMD should be considered for adults and pediatric patients who have a history of pathologic bone fracture or other risk factors for osteoporosis or bone loss. Although the effect of supplementation with calcium and vitamin D was not studied, such supplementation may be beneficial for all patients. If bone abnormalities are suspected then appropriate consultation should be obtained.
Mineralization Defects:
Cases of osteomalacia associated with proximal renal tubulopathy, manifested as bone pain or pain in extremities and which may contribute to fractures, have been reported in association with the use of tenofovir disoproxil fumarate tablets [See Adverse Reactions (6.2)].Arthralgias and muscle pain or weakness have also been reported in cases of proximal renal tubulopathy. Hypophosphatemia and osteomalacia secondary to proximal renal tubulopathy should be considered in patients at risk of renal dysfunction who present with persistent or worsening bone or muscle symptoms while receiving products containing tenofovir DF [See Warnings and Precautions (5.2)].

5.7 Immune Reconstitution Syndrome

Immune reconstitution syndrome has been reported in HIV-infected patients treated with combination antiretroviral therapy, including tenofovir disoproxil fumarate tablets. During the initial phase of combination antiretroviral treatment, patients whose immune system responds may develop an inflammatory response to indolent or residual opportunistic infections (such as Mycobacterium avium infection, cytomegalovirus, Pneumocystis jirovecii pneumonia [PCP], or tuberculosis), which may necessitate further evaluation and treatment.
Autoimmune disorders (such as Graves’ disease, polymyositis, and Guillain-Barré syndrome) have also been reported to occur in the setting of immune reconstitution; however, the time to onset is more variable, and can occur many months after initiation of treatment.

5.8 Early Virologic Failure

Clinical trials in HIV-infected subjects have demonstrated that certain regimens that only contain three nucleoside reverse transcriptase inhibitors (NRTI) are generally less effective than triple drug regimens containing two NRTIs in combination with either a non-nucleoside reverse transcriptase inhibitor or a HIV-1 protease inhibitor. In particular, early virological failure and high rates of resistance substitutions have been reported. Triple nucleoside regimens should therefore be used with caution. Patients on a therapy utilizing a triple nucleoside-only regimen should be carefully monitored and considered for treatment modification.

6 ADVERSE REACTIONS

The following adverse reactions are discussed in other sections of the labeling:
• Severe Acute Exacerbation of Hepatitis [See Boxed Warning, Warnings and Precautions (5.1)].
• New Onset or Worsening Renal Impairment [See Warnings and Precautions (5.2)].
• Lactic Acidosis/Severe Hepatomegaly with Steatosis [See Warnings and Precautions (5.3)].
• Bone Effects [See Warnings and Precautions (5.6)].
• Immune Reconstitution Syndrome [See Warnings and Precautions (5.7)].

6.1 Adverse Reactions from Clinical Trials Experience

Because clinical trials are conducted under widely varying conditions, adverse reaction rates observed in the clinical trials of a drug cannot be directly compared to rates in the clinical trials of another drug and may not reflect the rates observed in practice.
Clinical Trials in Adult Patients with HIV-1 Infection
More than 12,000 subjects have been treated with tenofovir disoproxil fumarate tablets alone or in combination with other antiretroviral medicinal products for periods of 28 days to 215 weeks in clinical trials and expanded access programs. A total of 1,544 subjects have received tenofovir disoproxil fumarate tablets 300 mg once daily in clinical trials; over 11,000 subjects have received tenofovir disoproxil fumarate tablets in expanded access programs.
The most common adverse reactions (incidence greater than or equal to 10%, Grades 2 to 4) identified from any of the 3 large controlled clinical trials include rash, diarrhea, headache, pain, depression, asthenia, and nausea.
Treatment-Naïve Patients
Study 903 - Treatment-Emergent Adverse-Reactions: The most common adverse reactions seen in a double-blind comparative controlled trial in which 600 treatment-naïve subjects received tenofovir disoproxil fumarate tablets (N=299) or stavudine (N=301) in combination with lamivudine and efavirenz for 144 weeks (Study 903) were mild to moderate gastrointestinal events and dizziness.

Mild adverse reactions (Grade 1) were common with a similar incidence in both arms and included dizziness, diarrhea, and nausea. Selected treatment-emergent moderate to severe adverse reactions are summarized in Table 4.

Table 4 Selected Treatment-Emergent Adverse Reactionsa (Grades 2 to 4) Reported in ≥5% in Any Treatment Group in Study 903 (0 to 144 Weeks)

 | Tenofovir disoproxil fumarate Tablets +3TC+EFV | d4T+3TC+EFV
 | N=299 | N=301
Body as a Whole Headache Pain Fever Abdominal pain Back pain Asthenia | 14% 13% 8% 7% 9% 6% | 17% 12% 7% 12% 8% 7%
Digestive System Diarrhea Nausea Dyspepsia Vomiting | 11% 8% 4% 5% | 13% 9% 5% 9%
Metabolic Disorders Lipodystrophyb | 1% | 8%
Musculoskeletal Arthralgia Myalgia | 5% 3% | 7% 5%
Nervous System Depression Insomnia Dizziness Peripheral neuropathyc Anxiety | 11% 5% 3% 1% 6% | 10% 8% 6% 5% 6%
Respiratory Pneumonia | 5% | 5%
Skin and Appendages Rash eventd | 18% | 12%

a. Frequencies of adverse reactions are based on all treatment-emergent adverse events, regardless of relationship to study drug.
b. Lipodystrophy represents a variety of investigator-described adverse events not a protocol-defined syndrome.
c. Peripheral neuropathy includes peripheral neuritis and neuropathy.
d. Rash event includes rash, pruritus, maculopapular rash, urticaria, vesiculobullous rash, and pustular rash.
Laboratory Abnormalities: With the exception of fasting cholesterol and fasting triglyceride elevations that were more common in the stavudine group (40% and 9%) compared with tenofovir disoproxil fumarate tablets (19% and 1%), respectively, laboratory abnormalities observed in this trial occurred with similar frequency in the tenofovir disoproxil fumarate tablets and stavudine treatment arms. A summary of Grades 3 to 4 laboratory abnormalities is provided in Table 5.
Table 5 Grades 3 to 4 Laboratory Abnormalities Reported in ≥1% of Tenofovir Disoproxil Fumarate-Treated Subjects in Study 903 (0 to 144 Weeks)

 | Tenofovir disoproxil fumarate Tablets+3TC+EFV | d4T+3TC+EFV
 | N=299 | N = 301
Any ≥ Grade 3 Laboratory Abnormality | 36% | 42%
Fasting Cholesterol (>240 mg/dL) | 19% | 40%
Creatine Kinase (M: >990 U/L; F: >845 U/L) | 12% | 12%
Serum Amylase (>175 U/L) | 9% | 8%
AST (M: >180 U/L; F: >170 U/L) | 5% | 7%
ALT (M: >215 U/L; F: >170 U/L) | 4% | 5%
Hematuria (>100 RBC/HPF) | 7% | 7%
Neutrophils (<750/mm^3) | 3% | 1%
Fasting Triglycerides (>750 mg/dL) | 1% | 9%

Study 934 – Treatment-Emergent Adverse Reactions: In Study 934, 511 antiretroviral-naïve subjects received either tenofovir disoproxil fumarate tablets + EMTRIVA® administered in combination with efavirenz (N=257) or zidovudine/lamivudine administered in combination with efavirenz (N=254). Adverse reactions observed in this trial were generally consistent with those seen in previous studies in treatment-experienced or treatment-naïve subjects (Table 6).
Changes in Bone Mineral Density
In HIV-1 infected adult subjects in Study 903, there was a significantly greater mean percentage decrease from baseline in BMD at the lumbar spine in subjects receiving tenofovir disoproxil fumarate tablets + lamivudine + efavirenz (-2.2% ± 3.9) compared with subjects receiving stavudine + lamivudine + efavirenz (-1% ± 4.6) through 144 weeks. Changes in BMD at the hip were similar between the two treatment groups (-2.8% ± 3.5 in the tenofovir disoproxil fumarate tablets group vs. -2.4% ± 4.5 in the stavudine group). In both groups, the majority of the reduction in BMD occurred in the first 24 to 48 weeks of the trial and this reduction was sustained through Week 144. Twenty-eight percent of tenofovir disoproxil fumarate tablets-treated subjects vs. 21% of the stavudine-treated subjects lost at least 5% of BMD at the spine or 7% of BMD at the hip. Clinically relevant fractures (excluding fingers and toes) were reported in 4 subjects in the tenofovir disoproxil fumarate tablets group and 6 subjects in the stavudine group. In addition, there were significant increases in biochemical markers of bone metabolism (serum bone-specific alkaline phosphatase, serum osteocalcin, serum C telopeptide, and urinary N telopeptide) and higher serum parathyroid hormone levels and 1,25 Vitamin D levels in the tenofovir disoproxil fumarate tablets group relative to the stavudine group; however, except for bone-specific alkaline phosphatase, these changes resulted in values that remained within the normal range [See Warnings and Precautions (5.6)].
Table 6 Selected Treatment-Emergent Adverse Reactionsa (Grades 2 to 4) Reported in ≥5% in Any Treatment Group in Study 934 (0 to 144 Weeks)

 | Tenofovir disoproxil fumarate Tabletsb+FTC+EFV | AZT/3TC+EFV
 | N=257 | N=254
Gastrointestinal Disorder Diarrhea Nausea Vomiting | 9% 9% 2% | 5% 7% 5%
General Disorders and Administration Site Condition Fatigue | 9% | 8%
Infections and Infestations Sinusitis Upper respiratory tract infections Nasopharyngitis | 8% 8% 5% | 4% 5% 3%
Nervous System Disorders Headache Dizziness | 6% 8% | 5% 7%
Psychiatric Disorders Depression Insomnia | 9% 5% | 7% 7%
Skin and Subcutaneous Tissue Disorders Rash eventc | 7% | 9%

a. Frequencies of adverse reactions are based on all treatment-emergent adverse events, regardless of relationship to study drug.
b. From Weeks 96 to 144 of the trial, subjects received TRUVADA with efavirenz in place of tenofovir disoproxil fumarate tablets + EMTRIVA with efavirenz.
c. Rash event includes rash, exfoliative rash, rash generalized, rash macular, rash maculopapular, rash pruritic, and rash vesicular.
Laboratory Abnormalities: Laboratory abnormalities observed in this trial were generally consistent with those seen in previous trials (Table 7).

Table 7 Significant Laboratory Abnormalities Reported in ≥1% of Subjects in Any Treatment Group in Study 934 (0 to 144 Weeks)

 | Tenofovir disoproxil fumaratea Tablets+FTC+EFV | AZT/3TC+EFV
 | N=257 | N=254
Any ≥ Grade 3 Laboratory Abnormality | 30% | 26%
Fasting Cholesterol (>240 mg/dL) | 22% | 24%
Creatine Kinase (M: >990 U/L; F: >845 U/L) | 9% | 7%
Serum Amylase (>175 U/L) | 8% | 4%
Alkaline Phosphatase (>550 U/L) | 1% | 0%
AST (M: >180 U/L; F: >170 U/L) | 3% | 3%
ALT (M: >215 U/L; F: >170 U/L) | 2% | 3%
Hemoglobin (<8 mg/dL) | 0% | 4%
Hyperglycemia (>250 mg/dL) | 2% | 1%
Hematuria (>75 RBC/HPF) | 3% | 2%
Glycosuria (³3+) | <1% | 1%
Neutrophils (<750/mm^3) | 3% | 5%
Fasting Triglycerides (>750 mg/dL) | 4% | 2%

a. From Weeks 96 to 144 of the trial, subjects received TRUVADA with efavirenz in place of tenofovir disoproxil fumarate tablets + EMTRIVA with efavirenz.
Treatment-Experienced Patients
Treatment-Emergent Adverse Reactions: The adverse reactions seen in treatment-experienced subjects were generally consistent with those seen in treatment-naïve subjects including mild to moderate gastrointestinal events, such as nausea, diarrhea, vomiting, and flatulence. Less than 1% of subjects discontinued participation in the clinical trials due to gastrointestinal adverse reactions (Study 907).
A summary of moderate to severe treatment-emergent adverse reactions that occurred during the first 48 weeks of Study 907 is provided in Table 8.
Table 8 Selected Treatment-Emergent Adverse Reactionsa (Grades 2 to 4) Reported in ≥3% in Any Treatment Group in Study 907 (0 to 48 Weeks)

 | Tenofovir disoproxil fumarate Tablets (N=3 68) (Week 0-2 4) | Placebo (N=1 82) (Week 0-2 4) | Tenofovir disoproxil fumarate Tablets (N=3 68) (Week 0-4 8) | Placebo C rosso ver to Tenofovir disoproxil fumarate Tablets (N=1 70) (Week 2 4-4 8)
Body as a Whole Asthenia Pain He ad a che Abdomi nal p ain Back pain Ch e st pain Fever | 7% 7% 5% 4% 3% 3% 2% | 6% 7% 5% 3% 3% 1% 2% | 11% 12% 8% 7% 4% 3% 4% | 1% 4% 2% 6% 2% 2% 2%
Dig estive System Diarr hea Na u s ea Vomiting Anorexia Dys pe psia Flatule nce | 11% 8% 4% 3% 3% 3% | 10% 5% 1% 2% 2% 1% | 16% 11% 7% 4% 4% 4% | 11% 7% 5% 1% 2% 1%
R espiratory Pneum onia | 2% | 0% | 3% | 2%
Ner vous S ys tem De pr ess ion Insomn ia Perip heral neuropathyb Dizzi ness | 4% 3% 3% 1% | 3% 2% 3% 3% | 8% 4% 5% 3% | 4% 4% 2% 1%
Skin and A ppend age R ash eventc Sweating | 5% 3% | 4% 2% | 7% 3% | 1% 1%
Musculoskeletal Myalgia | 3% | 3% | 4% | 1%
Metabol ic Wei ght loss | 2% | 1% | 4% | 2%

a. Frequencies of adverse reactions are based on all treatment-emergent adverse events, regardless of relationship to study drug.
b. Peripheral neuropathy includes peripheral neuritis and neuropathy.
c. Rash event includes rash, pruritus, maculopapular rash, urticaria, vesiculobullous rash, and pustular rash.
Laboratory Abnormalities: Laboratory abnormalities observed in this trial occurred with similar frequency in the tenofovir disoproxil fumarate tablets and placebo-treated groups. A summary of Grades 3 to 4 laboratory abnormalities is provided in Table 9.
Table 9 Grades 3 to 4 Laboratory Abnormalities Reported in ≥1% of Tenofovir Disoproxil Fumarate Tablets-Treated Subjects in Study 907 (0 to 48 Weeks)

 | Tenofovir disoproxil fumarate Tablets (N=3 68) (Week 0-2 4) | Placebo (N=1 82) (Week 0-2 4) | Tenofovir disoproxil fumarate Tablets (N=3 68) (Week 0-4 8) | Placebo Cro sso ver to Tenofovir disoproxil fumarate (N=170) (Week 24-48)
Any ≥ Gra de 3 Lab orat ory Abnor mality | 25% | 38% | 35% | 34%
Triglyceri des (> 750 mg/ dL) | 8% | 13% | 11% | 9%
Cr eatine Kin ase (M: >9 90 U/ L; F: >845 U/L) | 7% | 14% | 12% | 12%
Serum Amyl a se (>1 75 U/ L) | 6% | 7% | 7% | 6%
Glycosuria (≥ 3+) | 3% | 3% | 3% | 2%
AST (M: >180 U/L; F: >170 U/L) | 3% | 3% | 4% | 5%
ALT (M: >215 U/L; F: >170 U/L) | 2% | 2% | 4% | 5%
Serum Gl u c o se (>2 50 U/ L) | 2% | 4% | 3% | 3%
Neutrophi ls (<7 50/mm^3) | 1% | 1% | 2% | 1%

Clinical Trials in Pediatric Subjects 2 Years of Age and Older with HIV-1 Infection
Assessment of adverse reactions is based on two randomized trials (Studies 352 and 321) in 184 HIV-1 infected pediatric subjects (2 to less than 18 years of age) who received treatment with tenofovir disoproxil fumarate tablets (N=93) or placebo/active comparator (N=91) in combination with other antiretroviral agents for 48 weeks. The adverse reactions observed in subjects who received treatment with tenofovir disoproxil fumarate tablets were consistent with those observed in clinical trials in adults.
Eighty-nine pediatric subjects (2 to less than 12 years of age) received tenofovir disoproxil fumarate tablets in Study 352 for a median exposure of 104 weeks. Of these, 4 subjects discontinued from the trial due to adverse reactions consistent with proximal renal tubulopathy. Three of these 4 subjects presented with hypophosphatemia and also had decreases in total body or spine BMD Z score [See Warnings and Precautions (5.6)].
Changes in Bone Mineral Density:
Clinical trials in HIV-1 infected children and adolescents evaluated BMD changes. In Study 321 (12 to less than 18 years), the mean rate of BMD gain at Week 48 was less in the tenofovir disoproxil fumarate tablets compared to the placebo treatment group. Six tenofovir disoproxil fumarate tablets-treated subjects and one placebo-treated subject had significant (greater than 4%) lumbar spine BMD loss at Week 48. Changes from baseline BMD Z-scores were -0.341 for lumbar spine and -0.458 for total body in the 28 subjects who were treated with tenofovir disoproxil fumarate tablets for 96 weeks. In Study 352 (2 to less than 12 years), the mean rate of BMD gain in lumbar spine at Week 48 was similar between the tenofovir disoproxil fumarate tablets and the d4T or AZT treatment groups. Total body BMD gain was less in the tenofovir disoproxil fumarate tablets compared to the d4T or AZT treatment groups. One tenofovir disoproxil fumarate-treated subject and none of the d4T or AZT-treated subjects experienced significant (greater than 4%) lumbar spine BMD loss at Week 48. Changes from baseline in BMD Z scores were -0.012 for lumbar spine and -0.338 for total body in the 64 subjects who were treated with tenofovir disoproxil fumarate tablets for 96 weeks. In both trials, skeletal growth (height) appeared to be unaffected [See Warnings and Precautions (5.6)].
Clinical Trials in Adult Subjects with Chronic Hepatitis B and Compensated Liver Disease
Treatment-Emergent Adverse Reactions: In controlled clinical trials in 641 subjects with chronic hepatitis B (0102 and 0103), more subjects treated with tenofovir disoproxil fumarate tablets during the 48-week double-blind period experienced nausea: 9% with tenofovir disoproxil fumarate tablets versus 2% with HEPSERA. Other treatment-emergent adverse reactions reported in more than 5% of subjects treated with tenofovir disoproxil fumarate tablets included: abdominal pain, diarrhea, headache, dizziness, fatigue, nasopharyngitis, back pain, and skin rash.
During the open-label phase of treatment with tenofovir disoproxil fumarate tablets (weeks 48 to 384) in Studies 0102 and 0103, 2% of subjects (13/585) experienced a confirmed increase in serum creatinine of 0.5 mg/dL from baseline. No significant change in the tolerability profile was observed with continued treatment for up to 384 weeks.
Laboratory Abnormalities: A summary of Grades 3 to 4 laboratory abnormalities through Week 48 is provided in Table 10. Grades 3 to 4 laboratory abnormalities were similar in subjects continuing tenofovir disoproxil fumarate tablets treatment for up to 384 weeks in these trials.
Table 10 Grades 3 to 4 Laboratory Abnormalities Reported in ≥1% of Tenofovir disoproxil fumarate -Treated Subjects in Studies 0102 and 0103 (0 to 48 Weeks)

 | Tenofovir disoproxil fumarate Tablets (N=426) | HEPSERA (N=215)
Any ≥ Grade 3 Laboratory Abnormality | 19% | 13%
Creatine Kinase (M: >990 U/L; F: >845 U/L) | 2% | 3%
Serum Amylase (>175 U/L) | 4% | 1%
Glycosuria (≥3+) | 3% | <1%
AST (M: >180 U/L; F: >170 U/L) | 4% | 4%
ALT (M: >215 U/L; F: >170 U/L) | 10% | 6%

The overall incidence of on-treatment ALT flares (defined as serum ALT greater than 2 × baseline and greater than 10 × ULN, with or without associated symptoms) was similar between tenofovir disoproxil fumarate tablets (2.6%) and HEPSERA (2%). ALT flares generally occurred within the first 4 to 8 weeks of treatment and were accompanied by decreases in HBV DNA levels. No subject had evidence of decompensation. ALT flares typically resolved within 4 to 8 weeks without changes in study medication.
The adverse reactions observed in subjects with chronic hepatitis B and lamivudine resistance who received treatment with tenofovir disoproxil fumarate tablets were consistent with those observed in other hepatitis B clinical trials in adults.
Clinical Trials in Adult Subjects with Chronic Hepatitis B and Decompensated Liver Disease
In a small randomized, double-blind, active-controlled trial (0108), subjects with CHB and decompensated liver disease received treatment with tenofovir disoproxil fumarate tablets or other antiviral drugs for up to 48 weeks [See Clinical Studies (14.2)].Among the 45 subjects receiving tenofovir disoproxil fumarate tablets, the most frequently reported treatment-emergent adverse reactions of any severity were abdominal pain (22%), nausea (20%), insomnia (18%), pruritus (16%), vomiting (13%), dizziness (13%), and pyrexia (11%). Two of 45 (4%) subjects died through Week 48 of the trial due to progression of liver disease. Three of 45 (7%) subjects discontinued treatment due to an adverse event. Four of 45 (9%) subjects experienced a confirmed increase in serum creatinine of 0.5 mg/dL (1 subject also had a confirmed serum phosphorus less than 2 mg/dL through Week 48). Three of these subjects (each of whom had a Child-Pugh score greater than or equal to 10 and MELD score greater than or equal to 14 at entry) developed renal failure. Because both tenofovir disoproxil fumarate tablets and decompensated liver disease may have an impact on renal function, the contribution of tenofovir disoproxil fumarate tablets to renal impairment in this population is difficult to ascertain.
One of 45 subjects experienced an on-treatment hepatic flare during the 48-Week trial.
Clinical Trials in Pediatric Subjects 12 Years of Age and Older with Chronic Hepatitis B
Assessment of adverse reactions is based on one randomized study (Study GS-US-174-0115) in 106 pediatric subjects (12 to less than 18 years of age) infected with chronic hepatitis B receiving treatment with tenofovir disoproxil fumarate tablets (N=52) or placebo (N=54) for 72 weeks. The adverse reactions observed in pediatric subjects who received treatment with tenofovir disoproxil fumarate tablets were consistent with those observed in clinical trials of tenofovir disoproxil fumarate tablets in adults.
In this study, both the tenofovir disoproxil fumarate tablets and placebo treatment arms experienced an overall increase in mean lumbar spine BMD over 72 weeks, as expected for an adolescent population. The BMD gains from baseline to Week 72 in lumbar spine and total body BMD in tenofovir disoproxil fumarate-treated subjects (+5% and +3%, respectively) were less than the BMD gains observed in placebo-treated subjects (+8% and +5%, respectively). Three subjects in the tenofovir disoproxil fumarate tablets group and two subjects in the placebo group had significant (greater than 4%) lumbar spine BMD loss at Week 72. At baseline, mean BMD Z-scores in subjects randomized to tenofovir disoproxil fumarate tablets were −0.43 for lumbar spine and −0.20 for total body, and mean BMD Z-scores in subjects randomized to placebo were −0.28 for lumbar spine and −0.26 for total body. In subjects receiving tenofovir disoproxil fumarate tablets for 72 weeks, the mean change in BMD Z-score was −0.05 for lumbar spine and −0.15 for total body compared to +0.07 and +0.06, respectively, in subjects receiving placebo. As observed in pediatric studies of HIV-infected patients, skeletal growth (height) appeared to be unaffected [See Warnings and Precautions (5.6)].

6.2 Postmarketing Experience

The following adverse reactions have been identified during postapproval use of tenofovir disoproxil fumarate tablets. Because postmarketing reactions are reported voluntarily from a population of uncertain size, it is not always possible to reliably estimate their frequency or establish a causal relationship to drug exposure.
Immune System Disorders
allergic reaction, including angioedema
Metabolism and Nutrition Disorders
lactic acidosis, hypokalemia, hypophosphatemia
Respiratory, Thoracic, and Mediastinal Disorders
dyspnea
Gastrointestinal Disorders
pancreatitis, increased amylase, abdominal pain
Hepatobiliary Disorders
hepatic steatosis, hepatitis, increased liver enzymes (most commonly AST, ALT gamma GT)
Skin and Subcutaneous Tissue Disorders
rash
Musculoskeletal and Connective Tissue Disorders
rhabdomyolysis, osteomalacia (manifested as bone pain and which may contribute to fractures), muscular weakness, myopathy
Renal and Urinary Disorders
acute renal failure, renal failure, acute tubular necrosis, Fanconi syndrome, proximal renal tubulopathy, interstitial nephritis (including acute cases), nephrogenic diabetes insipidus, renal insufficiency, increased creatinine, proteinuria, polyuria
General Disorders and Administration Site Conditions
asthenia
The following adverse reactions, listed under the body system headings above, may occur as a consequence of proximal renal tubulopathy: rhabdomyolysis, osteomalacia, hypokalemia, muscular weakness, myopathy, hypophosphatemia.

To report SUSPECTED ADVERSE REACTIONS contact AvKARE at 1-855-361-3993; email drugsafety@avkare.com; or FDA at 1-800-FDA-1088 or www.fda.gov/medwatch.

7 DRUG INTERACTIONS

This section describes clinically relevant drug interactions with tenofovir disoproxil fumarate tablets. Drug interactions trials are described elsewhere in the labeling [See Clinical Pharmacology (12.3)].

7.1 Didanosine

Tenofovir is primarily eliminated by the kidneys [see Clinical Pharmacology (12.3)]. Coadministration of tenofovir disoproxil fumarate tablets with drugs that are eliminated by active tubular secretion may increase concentrations of tenofovir and/or the coadministered drug. Some examples include, but are not limited to, acyclovir, cidofovir, ganciclovir, valacyclovir, valganciclovir, aminoglycosides (e.g., gentamicin), and high-dose or multiple NSAIDs [see Warnings and Precautions (5.2)]. Drugs that decrease renal function may increase concentrations of tenofovir.
In the treatment of chronic hepatitis B, tenofovir disoproxil fumarate tablets should not be administered in combination with HEPSERA (adefovir dipivoxil).

7.2 HIV-1 Protease Inhibitors

Table 11 provides a listing of established or clinically significant drug interactions. The drug interactions described are based on studies conducted with tenofovir DF [see Clinical Pharmacology (12.3)].
Table 11 Established and Significanta Drug Interactions: Alteration in Dose or Regimen May Be Recommended Based on Drug Interaction Trials

Concomitant Drug Class: Drug Name | Effect on Concentrationb | Clinical Comment
NRTI: didanosine | ↑ didanosine | Patients receiving tenofovir disoproxil fumarate tablets and didanosine should be monitored closely for didanosine-associated adverse reactions. Discontinue didanosine in patients who develop didanosine-associated adverse reactions. Higher didanosine concentrations could potentiate didanosine-associated adverse reactions, including pancreatitis, and neuropathy. Suppression of CD4+ cell counts has been observed in patients receiving tenofovir disoproxil fumarate tablets with didanosine 400 mg daily. In patients weighing greater than 60 kg, reduce the didanosine dose to 250 mg when it is coadministered with tenofovir disoproxil fumarate tablets. In patients weighing less than 60 kg, reduce the didanosine dose to 200 mg when it is coadministered with tenofovir disoproxil fumarate tablets. When coadministered, tenofovir disoproxil fumarate tablets and Videx EC may be taken under fasted conditions or with a light meal (less than 400 kcal, 20% fat).
HIV-1 Protease Inhibitors:; atazanavir lopinavir/ritonavir atazanavir/ritonavir darunavir/ritonavir | ↓ atazanavir ↑ tenofovir | When coadministered with tenofovir disoproxil fumarate tablets, atazanavir 300 mg should be given with ritonavir 100 mg. Monitor patients receiving tenofovir disoproxil fumarate tablets concomitantly with lopinavir/ritonavir, ritonavir-boosted atazanavir, or ritonavir-boosted darunavir for tenofovir DF-associated adverse reactions. Discontinue tenofovir disoproxil fumarate tablets in patients who develop tenofovir DF-associated adverse reactions.
Hepatitis C Antiviral Agents: sofosbuvir/velpatasvir sofosbuvir/velpatasvir/ voxilaprevir ledipasvir/sofosbuvir | ↑ tenofovir | Monitor patients receiving tenofovir disoproxil fumarate tablets concomitantly with EPCLUSA® (sofosbuvir/velpatasvir) or VOSEVI® (sofosbuvir/velpatasvir/voxilaprevir) for adverse reactions associated with tenofovir DF. Monitor patients receiving tenofovir disoproxil fumarate tablets concomitantly with HARVONI® (ledipasvir/sofosbuvir) without an HIV-1 protease inhibitor/ritonavir or an HIV-1 protease inhibitor/cobicistat combination for adverse reactions associated with tenofovir DF. In patients receiving tenofovir disoproxil fumarate tablets concomitantly with HARVONI and an HIV-1 protease inhibitor/ritonavir or an HIV-1 protease inhibitor/cobicistat combination, consider an alternative HCV or antiretroviral therapy, as the safety of increased tenofovir concentrations in this setting has not been established. If coadministration is necessary, monitor for adverse reactions associated with tenofovir DF.

a. This table is not all inclusive.

b. ↑=Increase, ↓=Decrease

8 USE IN SPECIFIC POPULATIONS

8.1 Pregnancy

Pregnancy Category B
There are no adequate and well-controlled studies in pregnant women. Because animal reproduction studies are not always predictive of human response, tenofovir disoproxil fumarate tablets should be used during pregnancy only if clearly needed.
Antiretroviral Pregnancy Registry: To monitor fetal outcomes of pregnant women exposed to tenofovir disoproxil fumarate tablets, an Antiretroviral Pregnancy Registry has been established. Healthcare providers are encouraged to register patients by calling 1-800-258-4263.
Risk Summary
Animal Data
Reproduction studies have been performed in rats and rabbits at doses up to 14 and 19 times the human dose based on body surface area comparisons and revealed no evidence of impaired fertility or harm to the fetus due to tenofovir.

8.3 Nursing Mothers

Nursing Mothers: The Centers for Disease Control and Prevention recommend that HIV-1 infected mothers not breastfeed their infants to avoid risking postnatal transmission of HIV-1. Samples of breast milk obtained from five HIV-1 infected mothers in the first post-partum week show that tenofovir is secreted in human milk. The impact of this exposure in breastfed infants is unknown. Because of both the potential for HIV-1 transmission and the potential for serious adverse reactions in nursing infants, mothers should be instructed not to breastfeed if they are receiving tenofovir disoproxil fumarate tablets.

8.4 Pediatric Use

Pediatric Patients 2 Years of Age and Older with HIV-1 infection
The safety of tenofovir disoproxil fumarate tablets in pediatric patients aged 2 to less than 18 years is supported by data from two randomized trials in which tenofovir disoproxil fumarate tablets were administered to HIV-1 infected treatment-experienced subjects. In addition, the pharmacokinetic profile of tenofovir in patients 2 to less than 18 years of age at the recommended doses was similar to that found to be safe and effective in adult clinical trials [See Clinical Pharmacology (12.3)].
In Study 352, 92 treatment-experienced subjects 2 to less than 12 years of age with stable, virologic suppression on stavudine- or zidovudine-containing regimen were randomized to either replace stavudine or zidovudine with tenofovir disoproxil fumarate tablets (N=44) or continue their original regimen (N=48) for 48 weeks. Five additional subjects over the age of 12 were enrolled and randomized (tenofovir disoproxil fumarate tablets N=4, original regimen N=1) but are not included in the efficacy analysis. After 48 weeks, all eligible subjects were allowed to continue in the study receiving open-label tenofovir disoproxil fumarate tablets. At Week 48, 89% of subjects in the tenofovir disoproxil fumarate treatment group and 90% of subjects in the stavudine or zidovudine treatment group had HIV-1 RNA concentrations less than 400 copies/mL. During the 48 week randomized phase of the study, 1 subject in the tenofovir disoproxil fumarate tablets group discontinued the study prematurely because of virologic failure/lack of efficacy and 3 subjects (2 subjects in the tenofovir disoproxil fumarate tablets group and 1 subject in the stavudine or zidovudine group) discontinued for other reasons.
In Study 321, 87 treatment-experienced subjects 12 to less than 18 years of age were treated with tenofovir disoproxil fumarate tablets (N=45) or placebo (N=42) in combination with an optimized background regimen (OBR) for 48 weeks. The mean baseline CD4 cell count was 374 cells/mm^3 and the mean baseline plasma HIV-1 RNA was 4.6 log10 copies/mL. At baseline, 90% of subjects harbored NRTI resistance-associated substitutions in their HIV-1 isolates. Overall, the trial failed to show a difference in virologic response between the tenofovir disoproxil fumarate tablets and placebo treatment groups. Subgroup analyses suggest the lack of difference in virologic response may be attributable to imbalances between treatment arms in baseline viral susceptibility to tenofovir disoproxil fumarate tablets and OBR.
Although changes in HIV-1 RNA in these highly treatment-experienced subjects were less than anticipated, the comparability of the pharmacokinetic and safety data to that observed in adults supports the use of tenofovir disoproxil fumarate tablets in pediatric patients 12 years of age and older who weigh greater than or equal to 35 kg and whose HIV-1 isolate is expected to be sensitive to tenofovir disoproxil fumarate tablets. [See Warnings and Precautions (5.6), Adverse Reactions (6.1), and Clinical Pharmacology (12.3)].
Safety and effectiveness of tenofovir disoproxil fumarate tablets in pediatric patients younger than 2 years of age with HIV-1 infection have not been established.
Pediatric Patients 12 Years of Age and Older with Chronic Hepatitis B
In Study 115, 106 HBeAg negative (9%) and positive (91%) subjects aged 12 to less than 18 years with chronic HBV infection were randomized to receive blinded treatment with tenofovir disoproxil fumarate tablets 300 mg (N=52) or placebo (N=54) for 72 weeks. At study entry, the mean HBV DNA was 8.1 log10 copies/mL and mean ALT was 101 U/L. Of 52 subjects treated with tenofovir disoproxil fumarate tablets, 20 subjects were nucleos(t)ide-naïve and 32 subjects were nucleos(t)ide-experienced. Thirty-one of the 32 nucleos(t)ide-experienced subjects had prior lamivudine experience. At Week 72, 88% (46/52) of subjects in the tenofovir disoproxil fumarate tablets group and 0% (0/54) of subjects in the placebo group had HBV DNA <400 copies/mL (69 IU/mL). Among subjects with abnormal ALT at baseline, 74% (26/35) of subjects receiving tenofovir disoproxil fumarate tablets had normalized ALT at Week 72 compared to 31% (13/42) in the placebo group. One tenofovir disoproxil fumarate-treated subject experienced sustained HBsAg-loss and seroconversion to anti-HBs during the first 72 weeks of study participation.
Safety and effectiveness of tenofovir disoproxil fumarate tablets in pediatric patients younger than 12 years of age or less than 35 kg with chronic hepatitis B have not been established.

8.5 Geriatric Use

Clinical trials of tenofovir disoproxil fumarate tablets did not include sufficient numbers of subjects aged 65 and over to determine whether they respond differently from younger subjects. In general, dose selection for the elderly patient should be cautious, keeping in mind the greater frequency of decreased hepatic, renal, or cardiac function, and of concomitant disease or other drug therapy.

8.6 Patients with Impaired Renal Function

It is recommended that the dosing interval for tenofovir disoproxil fumarate tablets be modified in patients with estimated creatinine clearance below 50 mL/min or in patients with ESRD who require dialysis [See Dosage and Administration (2.3),Clinical Pharmacology (12.3)].

10 OVERDOSAGE

Limited clinical experience at doses higher than the therapeutic dose of tenofovir disoproxil fumarate tablets 300 mg are available. In Study 901, 600 mg tenofovir DF was administered to 8 subjects orally for 28 days. No severe adverse reactions were reported. The effects of higher doses are not known.
If overdose occurs the patient must be monitored for evidence of toxicity and standard supportive treatment applied as necessary.
Tenofovir is efficiently removed by hemodialysis with an extraction coefficient of approximately 54%. Following a single 300 mg dose of tenofovir disoproxil fumarate tablets, a four-hour hemodialysis session removed approximately 10% of the administered tenofovir dose.

11 DESCRIPTION

Tenofovir disoproxil fumarate tablet a prodrug of tenofovir which is a fumaric acid salt of bis-isopropoxycarbonyloxymethyl ester derivative of tenofovir. In vivo tenofovir DF is converted to tenofovir, an acyclic nucleoside phosphonate (nucleotide) analog of adenosine 5’-monophosphate. Tenofovir exhibits activity against HIV-1 reverse transcriptase.
The chemical name of tenofovir DF is 9-[(R)-2-[[bis[[(isopropoxycarbonyl)oxy]methoxy]phosphinyl]methoxy]propyl] adenine fumarate (1:1). It has a molecular formula of C19H30N5O10P • C4H4O4 and a molecular weight of 635.52. It has the following structural formula:

Tenofovir DF is a white to off-white crystalline powder with a solubility of 13.4 mg/mL in distilled water at 25°C. It has an octanol/phosphate buffer (pH 6.5) partition coefficient (log p) of 1.25 at 25 °C.
Tenofovir disoproxil fumarate is available as tablets.
Tenofovir disoproxil fumarate tablets are for oral administration. Each tablet contains 300 mg of tenofovir DF, which is equivalent to 245 mg of tenofovir disoproxil. Each tablet contains the following inactive ingredients: croscarmellose sodium, lactose monohydrate, magnesium stearate, microcrystalline cellulose and pregelatinized starch. The 300 mg tablets are coated with opadry II white which contains hypromellose, lactose monohydrate, titanium dioxide and triacetin.
In this insert, all dosages are expressed in terms of tenofovir DF except where otherwise noted.

12 CLINICAL PHARMACOLOGY

12.1 Mechanism of Action

Tenofovir disoproxil fumarate is an antiviral drug [See Microbiology (12.4)].

12.3 Pharmacokinetics

The pharmacokinetics of tenofovir DF have been evaluated in healthy volunteers and HIV-1 infected individuals. Tenofovir pharmacokinetics are similar between these populations.
Absorption
Tenofovir disoproxil fumarate tablets are a water soluble diester prodrug of the active ingredient tenofovir. The oral bioavailability of tenofovir from tenofovir disoproxil fumarate tablets in fasted subjects is approximately 25%. Following oral administration of a single dose of tenofovir disoproxil fumarate tablets 300 mg to HIV-1 infected subjects in the fasted state, maximum serum concentrations (Cmax) are achieved in 1 ± 0.4 hrs. Cmax and AUC values are 0.30 ± 0.09 mcg/mL and 2.29 ± 0.69 mcg·hr/mL, respectively.
The pharmacokinetics of tenofovir are dose proportional over a tenofovir disoproxil fumarate tablets dose range of 75 to 600 mg and are not affected by repeated dosing.
Distribution
In vitro binding of tenofovir to human plasma or serum proteins is less than 0.7 and 7.2%, respectively, over the tenofovir concentration range 0.01 to 25 mcg/mL. The volume of distribution at steady-state is 1.3 ± 0.6 L/kg and 1.2 ± 0.4 L/kg, following intravenous administration of tenofovir 1 mg/kg and 3 mg/kg.
Metabolism and Elimination
In vitro studies indicate that neither tenofovir disoproxil nor tenofovir are substrates of CYP enzymes.
Following IV administration of tenofovir, approximately 70 to 80% of the dose is recovered in the urine as unchanged tenofovir within 72 hours of dosing. Following single dose, oral administration of tenofovir disoproxil fumarate tablets, the terminal elimination half-life of tenofovir is approximately 17 hours. After multiple oral doses of tenofovir disoproxil fumarate tablets 300 mg once daily (under fed conditions), 32 ± 10% of the administered dose is recovered in urine over 24 hours.
Tenofovir is eliminated by a combination of glomerular filtration and active tubular secretion. There may be competition for elimination with other compounds that are also renally eliminated.
Effects of Food on Oral Absorption
Administration of tenofovir disoproxil fumarate 300 mg tablets following a high-fat meal (~700 to 1,000 kcal containing 40 to 50% fat) increases the oral bioavailability, with an increase in tenofovir AUC0 to ∞ of approximately 40% and an increase in Cmax of approximately 14%. However, administration of tenofovir disoproxil fumarate tablets with a light meal did not have a significant effect on the pharmacokinetics of tenofovir when compared to fasted administration of the drug. Food delays the time to tenofovir Cmax by approximately 1 hour. Cmax and AUC of tenofovir are 0.33 ± 0.12 mcg/mL and 3.32 ± 1.37 mcg·hr/mL following multiple doses of tenofovir disoproxil fumarate tablets 300 mg once daily in the fed state, when meal content was not controlled.
Special Populations
Race: There were insufficient numbers from racial and ethnic groups other than Caucasian to adequately determine potential pharmacokinetic differences among these populations.
Gender: Tenofovir pharmacokinetics are similar in male and female subjects.
Pediatric Patients 2 Years of Age and Older: Steady-state pharmacokinetics of tenofovir were evaluated in 31 HIV-1 infected pediatric subjects 2 to less than 18 years (Table 12). Tenofovir exposure achieved in these pediatric subjects receiving oral once daily doses of tenofovir disoproxil fumarate tablets 300 mg up to a maximum dose of 300 mg was similar to exposures achieved in adults receiving once-daily doses of tenofovir disoproxil fumarate tablets 300 mg.
Table 12 Mean (± SD) Tenofovir Pharmacokinetic Parameters by Age Groups for HIV-1- infected Pediatric Patients

Dose and Formulation | 300 mg tablet
 | 12 to <18 Years (N=8)
Cmax (mcg/mL) | 0.38 ± 0.13
AUCtau (mcg•hr/mL) | 3.39 ± 1.22

Tenofovir exposures in 52 HBV-infected pediatric subjects (12 to less than 18 years of age) receiving oral once-daily doses of tenofovir disoproxil fumarate 300 mg tablet were comparable to exposures achieved in HIV-1 infected adults and adolescents receiving once-daily doses of 300 mg.
Geriatric Patients: Pharmacokinetic trials have not been performed in the elderly (65 years and older).
Patients with Impaired Renal Function: The pharmacokinetics of tenofovir are altered in subjects with renal impairment [See Warnings and Precautions (5.2)].In subjects with creatinine clearance below 50 mL/min or with end-stage renal disease (ESRD) requiring dialysis, Cmax, and AUC 0 to ∞ of tenofovir were increased (Table 13). It is recommended that the dosing interval for tenofovir disoproxil fumarate tablets be modified in patients with estimated creatinine clearance below 50 mL/min or in patients with ESRD who require dialysis [See Dosage and Administration (2.3)].
Table 13 Pharmacokinetic Parameters (Mean ± SD) of Tenofovira in Subjects with Varying Degrees of Renal Function

Baseline Creatinine Clearance (mL/min) | >80 (N=3) | 50-80 (N=10) | 30-49 (N=8) | 12-29 (N=11)
Cmax(mcg/mL) | 0.34 ± 0.03 | 0.33 ± 0.06 | 0.37 ± 0.16 | 0.60 ± 0.19
AUC0 to∞ (mcg ·hr/mL) | 2.18 ± 0.26 | 3.06 ± 0.93 | 6.01 ± 2.50 | 15.98 ± 7.22
CL/F (mL/min) | 1043.7 ± 115.4 | 807.7 ± 279.2 | 444.4 ± 209.8 | 177 ± 97.1
CLrenal (mL/min) | 243.5 ± 33.3 | 168.6 ± 27.5 | 100.6 ± 27.5 | 43 ± 31.2

a. 300 mg, single dose of tenofovir disoproxil fumarate tablets
Tenofovir is efficiently removed by hemodialysis with an extraction coefficient of approximately 54%. Following a single 300 mg dose of tenofovir disoproxil fumarate tablets, a four-hour hemodialysis session removed approximately 10% of the administered tenofovir dose.
Patients with Hepatic Impairment: The pharmacokinetics of tenofovir following a 300 mg single dose of tenofovir disoproxil fumarate tablets have been studied in non-HIV infected subjects with moderate to severe hepatic impairment. There were no substantial alterations in tenofovir pharmacokinetics in subjects with hepatic impairment compared with unimpaired subjects. No change in tenofovir disoproxil fumarate tablets dosing is required in patients with hepatic impairment.
Assessment of Drug Interactions
At concentrations substantially higher (~300-fold) than those observed in vivo, tenofovir did not inhibit in vitro drug metabolism mediated by any of the following human CYP isoforms: CYP3A4, CYP2D6, CYP2C9, or CYP2E1. However, a small (6%) but statistically significant reduction in metabolism of CYP1A substrate was observed. Based on the results of in vitro experiments and the known elimination pathway of tenofovir, the potential for CYP-mediated interactions involving tenofovir with other medicinal products is low.
Tenofovir disoproxil fumarate tablets have been evaluated in healthy volunteers in combination with other antiretroviral and potential concomitant drugs. Tables 14 and 15 summarize pharmacokinetic effects of coadministered drug on tenofovir pharmacokinetics and effects of tenofovir disoproxil fumarate tablets on the pharmacokinetics of coadministered drug.
TDF is a substrate of P-glycoprotein (P-gp) and breast cancer resistance protein (BCRP) transporters. When TDF is coadministered with an inhibitor of these transporters, an increase in absorption may be observed.
No clinically significant drug interactions have been observed between tenofovir disoproxil fumarate tablets and efavirenz, methadone, nelfinavir, oral contraceptives, ribavirin, or sofosbuvir.
Table 14 Drug Interactions: Changes in Pharmacokinetic Parameters for Tenofovira in the Presence of the Coadministered Drug

Coadministered Drug | Dose of Coadministered Drug (mg) | N | % Change of Tenofovir Pharmacokinetic Parametersb (90% CI)
Coadministered Drug | Dose of Coadministered Drug (mg) | N | Cmax | AUC | Cmin
Atazanavirc | 400 once daily × 14 days | 33 | ↑ 14 (↑ 8 to ↑ 20) | ↑ 24 (↑ 21 to ↑ 28) | ↑ 22 (↑ 15 to ↑ 30)
Atazanavir/ Ritonavirc | 300/100 once daily | 12 | ↑ 34 (↑ 20 to ↑ 51) | ↑ 37 (↑ 30 to ↑ 45) | ↑ 29 (↑ 21 to ↑ 36)
Darunavir/ Ritonavird | 300/100 twice daily | 12 | ↑ 24 (↑ 8 to ↑ 42) | ↑ 22 (↑ 10 to ↑ 35) | ↑ 37 (↑ 19 to ↑ 57)
Indinavir | 800 three times daily × 7 days | 13 | ↑ 14 (↓ 3 to ↑ 33) | Û | Û
Ledipasvir/ Sofosbuvire,f | 90/400 once daily x 10 days | 24 | ↑ 47 (↑ 37 to ↑ 58) | ↑ 35 (↑ 29 to ↑ 42) | ↑ 47 (↑ 38 to ↑ 57)
Ledipasvir/ Sofosbuvire,g | 90/400 once daily x 10 days | 23 | ↑ 64 (↑ 54 to ↑ 74) | ↑ 50 (↑ 42 to ↑ 59) | ↑ 59 (↑ 49 to ↑ 70)
Ledipasvir/ Sofosbuvirh | 90/400 once daily x 14 days | 15 | ↑ 79 (↑ 56 to ↑ 104) | ↑ 98 (↑ 77 to ↑ 123) | ↑ 163 (↑ 132 to ↑197)
Lopinavir/ Ritonavir | 400/100 twice daily × 14 days | 24 | Û | ↑ 32 (↑ 25 to ↑ 38) | ↑ 51 (↑ 37 to ↑ 66)
Saquinavir/ Ritonavir | 1,000/100 twice daily × 14 days | 35 | Û | Û | ↑ 23 (↑ 16 to ↑ 30)
Sofosbuviri | 400 single dose | 16 | ↑ 25 (↑ 8 to ↑ 45) | Û | Û
Sofosbuvir/ Velpatasvirj | 400/100 once daily | 24 | ↑ 44 (↑ 33 to ↑ 55) | ↑ 40 (↑ 34 to ↑ 46) | ↑ 84 (↑ 76 to ↑ 92)
Sofosbuvir/ Velpatasvirk | 400/100 once daily | 30 | ↑ 46 (↑ 39 to ↑ 54) | ↑ 40 (↑ 34 to ↑ 45) | ↑ 70 (↑ 61 to ↑ 79)
Sofosbuvir/ Velpatasvir/ Voxilaprevirl | 400/100/100 + Voxilaprevirm 100 once daily | 29 | ↑ 48 (↑ 36 to ↑ 61) | ↑ 39 (↑ 32 to↑ 46) | ↑ 47 (↑ 38 to ↑ 56)
Tacrolimus | 0.05 mg/kg twice Daily × 7 days | 21 | ↑ 13 (↑ 1 to ↑ 27) | Û | Û
Tipranavir/ Ritonavirn | 500/100 twice daily | 22 | ↓ 23 (↓ 32 to ↓ 13) | ↓ 2 (↓ 9 to ↑ 5) | ↑ 7 (↓ 2 to ↑ 17)
Tipranavir/ Ritonavirn | 750/200 twice daily (23 doses) | 20 | ↓ 38 (↓ 46 to ↓ 29) | ↑ 2 (↓ 6 to ↑ 10) | ↑ 14 (↑ 1 to ↑ 27)

a. Subjects received tenofovir disoproxil fumarate tablets 300 mg once daily.
b. Increase = ↑; Decrease = ↓; No Effect = Û
c. Reyataz Prescribing Information.
d. Prezista Prescribing Information.
e Data generated from simultaneous dosing with HARVONI (ledipasvir/sofosbuvir). Staggered administration (12 hours apart) provided similar results.
f. Comparison based on exposures when administered as atazanavir/ritonavir + emtricitabine/tenofovir DF.
g. Comparison based on exposures when administered as darunavir/ritonavir + emtricitabine/tenofovir DF.
h. Study conducted with ATRIPLA (efavirenz/emtricitabine/tenofovir DF) coadministered with HARVONI; coadministration with HARVONI also results in comparable increases in tenofovir exposure when TDF is administered as COMPLERA, or TRUVADA + dolutegravir.
i. Study conducted with ATRIPLA coadministered with SOVALDI® (sofosbuvir).
j. Study conducted with COMPLERA coadministered with EPCLUSA; coadministration with EPCLUSA also results in comparable increases in tenofovir exposures when TDF is administered as ATRIPLA, STRIBILD, TRUVADA + atazanavir/ritonavir, or TRUVADA + darunavir/ritonavir.
k. Administered as raltegravir + emtricitabine/tenofovir DF.
l. Comparison based on exposures when administered as darunavir/ritonavir + emtricitabine/tenofovir DF.
m. Study conducted with additional voxilaprevir 100 mg to achieve voxilaprevir exposures expected in HCV-infected patients.
n. Aptivus Prescribing Information.

No effect on the pharmacokinetic parameters of the following coadministered drugs was observed with tenofovir disoproxil fumarate: abacavir, didanosine (buffered tablets), emtricitabine, entecavir, and lamivudine.

Table 15 Drug Interactions: Changes in Pharmacokinetic Parameters for Coadministered Drug in the Presence of Tenofovir disoproxil fumarate Tablets

Coadministered Drug | Dose of Coadministered Drug (mg) | N | % Change of Coadministered Drug Pharmacokinetic Parametersa (90% CI)
Coadministered Drug | Dose of Coadministered Drug (mg) | N | Cmax | AUC | Cmin
Abacavir | 300 once | 8 | 12 (¯ 1 to 26) | Û | NA
Atazanavirb | 400 once daily x 14 days | 34 | ¯21 (¯27 to ¯ 14) | ¯25 (¯30 to ¯19) | ¯ 40 (¯ 48 to ¯ 32)
Atazanavirb | Atazanavir/Ritonavir 300/100 once daily x 42 days | 10 | ¯28 (¯ 50 to 5) | ¯25c (¯42 to ¯ 3) | ¯23c (¯46 to 10)
Darunavird | Darunavir/Ritonavir 300/100 once daily | 12 | 16 (¯ to 42) | 21 (¯ to 54) | 24 (¯ to 69)
Didanosinee | 250 once, simultaneously with tenofovir disoproxil fumarate tablets and a light mealf | 33 | ¯ 20g (¯ 32 to ¯ 7) | Ûg | NA
Emtricitabine | 200 once daily x 7 days | 17 | Û | Û | 20 (12 to 29)
Entecavir | 1 mg once daily x 10 days | 28 | Û | 13 (to 15) | Û
Indinavir | 800 three times daily x 7 days | 12 | ¯ 11 (¯ 30 to 12) | Û | Û
Lamivudine | 150 twice daily x 7 days | 15 | 24 (¯ 34 to ¯ 12) | Û | Û
Lopinavir Ritonavir | Lopinavir/Ritonavir 400/100 twice daily x 14 days | 24 | Û Û | Û Û | Û Û
Saquinavir Ritonavir | Saquinavir/Ritonavir 1,000/100 twice daily x 14 days | 32 | 22 (6 to 41) Û | 29h (12 to 48) Û | 47h (23 to 76) 23 (3 to 46)
Tacrolimus | 0.05 mg/kg twice daily x 7 days | 21 | Û | Û | Û
Tipranaviri | Tipranavir/Ritonavir 500/100 twice daily | 22 | ¯ 17 (¯ 26 to¯ 6) | ¯ 18 (¯ 25 to ¯ 9) | ¯ 21 (¯ 30 to ¯ 10)
Tipranaviri | Tipranavir/Ritonavir 750/200 twice daily (23 doses) | 20 | ¯ 11 (¯ 16 to ¯ 4) | ¯ 9 (¯ 15 to ¯ 3) | ¯ 12 (¯ 22 to0)

a. Increase = ↑; Decrease = ↓; No Effect = Û; NA = Not Applicable
b. Reyataz Prescribing Information.
c. In HIV-infected subjects, addition of tenofovir DF to atazanavir 300 mg plus ritonavir 100 mg, resulted in AUC and Cmin values of atazanavir that were 2.3- and 4-fold higher than the respective values observed for atazanavir 400 mg when given alone.
d. Prezista Prescribing Information.
e. Videx EC Prescribing Information. Subjects received didanosine enteric-coated capsules.
f. 373 kcal, 8.2 g fat
g. Compared with didanosine (enteric-coated) 400 mg administered alone under fasting conditions.
h. Increases in AUC and Cmin are not expected to be clinically relevant; hence no dose adjustments are required when tenofovir DF and ritonavir-boosted saquinavir are coadministered.
i. Aptivus Prescribing Information.

12.4 Microbiology

Mechanism of Action
Tenofovir DF is an acyclic nucleoside phosphonate diester analog of adenosine monophosphate. Tenofovir DF requires initial diester hydrolysis for conversion to tenofovir and subsequent phosphorylations by cellular enzymes to form tenofovir diphosphate, an obligate chain terminator. Tenofovir diphosphate inhibits the activity of HIV-1 reverse transcriptase and HBV reverse transcriptase by competing with the natural substrate deoxyadenosine 5'-triphosphate and, after incorporation into DNA, by DNA chain termination. Tenofovir diphosphate is a weak inhibitor of mammalian DNA polymerases α, β, and mitochondrial DNA polymerase γ.
Activity against HIV
Antiviral Activity
The antiviral activity of tenofovir against laboratory and clinical isolates of HIV-1 was assessed in lymphoblastoid cell lines, primary monocyte/macrophage cells and peripheral blood lymphocytes. The EC50 (50% effective concentration) values for tenofovir were in the range of 0.04 μM to 8.5 μM. In drug combination studies, tenofovir was not antagonistic with nucleoside reverse transcriptase inhibitors (abacavir, didanosine, lamivudine, stavudine, zalcitabine, zidovudine), non-nucleoside reverse transcriptase inhibitors (delavirdine, efavirenz, nevirapine), and protease inhibitors (amprenavir, indinavir, nelfinavir, ritonavir, saquinavir). Tenofovir displayed antiviral activity in cell culture against HIV-1 clades A, B, C, D, E, F, G, and O (EC50 values ranged from 0.5 μM to 2.2 μM) and strain-specific activity against HIV-2 (EC50 values ranged from 1.6 μM to 5.5 μM).
Resistance
HIV-1 isolates with reduced susceptibility to tenofovir have been selected in cell culture. These viruses expressed a K65R substitution in reverse transcriptase and showed a 2- to 4- fold reduction in susceptibility to tenofovir. In addition, a K70E substitution in HIV-1 reverse transcriptase has been selected by tenofovir and results in low-level reduced susceptibility to tenofovir.
In Study 903 of treatment-naïve subjects (tenofovir disoproxil fumarate tablets + lamivudine + efavirenz versus stavudine + lamivudine + efavirenz) [See Clinical Studies (14.1)], genotypic analyses of isolates from subjects with virologic failure through Week 144 showed development of efavirenz and lamivudine resistance-associated substitutions to occur most frequently and with no difference between the treatment arms. The K65R substitution occurred in 8/47 (17%) of analyzed patient isolates in the tenofovir disoproxil fumarate tablets arm and in 2/49 (4%) of analyzed patient isolates in the stavudine arm. Of the 8 subjects whose virus developed K65R in the tenofovir disoproxil fumarate tablets arm through 144 weeks, 7 occurred in the first 48 weeks of treatment and one at Week 96. One patient in the tenofovir disoproxil fumarate arm developed the K70E substitution in the virus. Other substitutions resulting in resistance to tenofovir disoproxil fumarate tablets were not identified in this trial.
In Study 934 of treatment-naïve subjects (tenofovir disoproxil fumarate tablets + EMTRIVA + efavirenz versus zidovudine (AZT)/lamivudine (3TC) + efavirenz) [See Clinical Studies (14.1)],genotypic analysis performed on HIV-1 isolates from all confirmed virologic failure subjects with greater than 400 copies/mL of HIV-1 RNA at Week 144 or early discontinuation showed development of efavirenz resistance-associated substitutions occurred most frequently and was similar between the two treatment arms. The M184V substitution, associated with resistance to EMTRIVA and lamivudine, was observed in 2/19 of analyzed subject isolates in the tenofovir disoproxil fumarate tablets + EMTRIVA group and in 10/29 of analyzed subject isolates in the zidovudine/lamivudine group. Through 144 weeks of Study 934, no subjects have developed a detectable K65R substitution in their HIV-1 as analyzed through standard genotypic analysis.
Cross Resistance
Cross-resistance among certain reverse transcriptase inhibitors has been recognized. The K65R and K70E substitutions selected by tenofovir are also selected in some HIV-1 infected subjects treated with abacavir or didanosine. HIV-1 isolates with this substitution also show reduced susceptibility to emtricitabine and lamivudine. Therefore, cross resistance among these drugs may occur in patients whose virus harbors the K65R or K70E substitution. HIV-1 isolates from subjects (N=20) whose HIV-1 expressed a mean of three zidovudine-associated reverse transcriptase substitutions (M41L, D67N, K70R, L210W, T215Y/F, or K219Q/E/N), showed a 3.1-fold decrease in the susceptibility to tenofovir.
In Studies 902 and 907 conducted in treatment-experienced subjects (tenofovir disoproxil fumarate tablets + Standard Background Therapy (SBT) compared to placebo + SBT) [See Clinical Studies (14.1)],14/304 (5%) of the tenofovir disoproxil fumarate-treated subjects with virologic failure through Week 96 had greater than 1.4-fold (median 2.7-fold) reduced susceptibility to tenofovir. Genotypic analysis of the baseline and failure isolates showed the development of the K65R substitution in the HIV-1 reverse transcriptase gene.
The virologic response to tenofovir disoproxil fumarate tablets therapy has been evaluated with respect to baseline viral genotype (N=222) in treatment-experienced subjects participating in Studies 902 and 907. In these clinical trials, 94% of the participants evaluated had baseline HIV-1 isolates expressing at least one NRTI substitution. Virologic responses for subjects in the genotype substudy were similar to the overall trial results.
Several exploratory analyses were conducted to evaluate the effect of specific substitutions and substitutional patterns on virologic outcome. Because of the large number of potential comparisons, statistical testing was not conducted. Varying degrees of cross resistance of tenofovir disoproxil fumarate tablets to pre-existing zidovudine resistance-associated substitutions (M41L, D67N, K70R, L210W, T215Y/F, or K219Q/E/N) were observed and appeared to depend on the type and number of specific substitutions. Tenofovir disoproxil fumarate tablets-treated subjects whose HIV-1 expressed 3 or more zidovudine resistance-associated substitutions that included either the M41L or L210W reverse transcriptase substitution showed reduced responses to tenofovir disoproxil fumarate tablets therapy; however, these responses were still improved compared with placebo. The presence of the D67N, K70R, T215Y/F, or K219Q/E/N substitution did not appear to affect responses to tenofovir disoproxil fumarate tablets therapy. Subjects whose virus expressed an L74V substitution without zidovudine resistance associated substitutions (N=8) had reduced response to tenofovir disoproxil fumarate tablets. Limited data are available for subjects whose virus expressed a Y115F substitution (N=3), Q151M substitution (N=2), or T69 insertion (N=4), all of whom had a reduced response.
In the protocol defined analyses, virologic response to tenofovir disoproxil fumarate tablets was not reduced in subjects with HIV-1 that expressed the abacavir/emtricitabine/lamivudine resistance-associated M184V substitution. HIV-1 RNA responses among these subjects were durable through Week 48.
Studies 902 and 907 Phenotypic Analyses
Phenotypic analysis of baseline HIV-1 from treatment-experienced subjects (N=100) demonstrated a correlation between baseline susceptibility to tenofovir disoproxil fumarate tablets and response to tenofovir disoproxil fumarate tablets therapy. Table 16 summarizes the HIV-1 RNA response by baseline tenofovir disoproxil fumarate tablets susceptibility.
Table 16 HIV-1 RNA Response at Week 24 by Baseline Tenofovir disoproxil fumarate Tablets Susceptibility (Intent-To-Treat)a

Baseline Tenofovir disoproxil fumarate Tablets Susceptibilityb | Change in HIV-1 RNAc (N)
<1 >1 and ≤3 >3 and ≤4 >4 | -0.74 (35) -0.56 (49) -0.3 (7) -0.12 (9)

a. Tenofovir susceptibility was determined by recombinant phenotypic Antivirogram assay (Virco).
b. Fold change in susceptibility from wild-type.
c. Average HIV-1 RNA change from baseline through Week 24 (DAVG24) in log10 copies/mL.
Activity against HBV
Antiviral Activity
The antiviral activity of tenofovir against HBV was assessed in the HepG2 2.2.15 cell line. The EC50 values for tenofovir ranged from 0.14 to 1.5 μM, with CC50 (50% cytotoxicity concentration) values greater than 100 μM. In cell culture combination antiviral activity studies of tenofovir with the nucleoside HBV reverse transcriptase inhibitors entecavir, lamivudine, and telbivudine, and with the nucleoside HIV-1 reverse transcriptase inhibitor emtricitabine, no antagonistic activity was observed.
Resistance
Cumulative tenofovir disoproxil fumarate tablets genotypic resistance has been evaluated annually for up to 384 weeks in Studies 0102, 0103, 0106, 0108 and 0121 with the paired HBV reverse transcriptase amino acid sequences of the pretreatment and on-treatment isolates from subjects who received at least 24 weeks of tenofovir disoproxil fumarate tablets monotherapy and remained viremic with HBV DNA greater than or equal to 400 copies/mL (69 IU/mL) at the end of each study year (or at discontinuation of tenofovir disoproxil fumarate tablets monotherapy) using an as-treated analysis. In the nucleotide-naïve population from Studies 0102 and 0103, HBeAg-positive subjects had a higher baseline viral load than HBeAg-negative subjects and a significantly higher proportion of the subjects remained viremic at their last time point on tenofovir disoproxil fumarate tablets monotherapy (15% versus 5%, respectively).
HBV isolates from these subjects who remained viremic showed treatment-emergent substitutions (Table 17); however, no specific substitutions occurred at a sufficient frequency to be associated with resistance to tenofovir disoproxil fumarate tablets (genotypic and phenotypic analyses).
Table 17 Amino Acid Substitutions in Viremic Subjects across HBV Trials of Tenofovir disoproxil fumarate Tablets

 | Compensated Liver Disease |  |  | Decompensated Liver Disease (N=39)d
 | Nucleotide-Naïve (N=417)a | HEPSERA-Experienced (N=247)b | Lamivudine-Resistant (N=136)C | Decompensated Liver Disease (N=39)d
Viremic at Last Time Point on Tenofovir disoproxil fumarate Tablets | 38/417 (9%) | 37/247 (15%) | 9/136 (7%) | 7/39 (18%)
Treatment-Emergent Amino Acid Substitutionse | 18f/32 (56%) | 11g/31 (35%) | 6h/8 (75%) | 3/5 (60%)

a. Nucleotide-naïve subjects from Studies 0102 (N=246) and 0103 (N=171) receiving up to 384 weeks of treatment with tenofovir disoproxil fumarate tablets.
b. HEPSERA-experienced subjects from Studies 0102/0103 (N=195) and 0106 (N=52) receiving up to 336 weeks of treatment with tenofovir disoproxil fumarate tablets after switching to tenofovir disoproxil fumarate tablets from HEPSERA. Study 0106, a randomized, double-blind, 168-week Phase 2 trial, has been completed.
c. Lamivudine-resistant subjects from Study 0121 (N=136) receiving up to 96 weeks of treatment with tenofovir disoproxil fumarate tablets after switching to tenofovir disoproxil fumarate tablets from lamivudine.
d. Subjects with decompensated liver disease from Study 0108 (N=39) receiving up to 48 weeks of treatment with tenofovir disoproxil fumarate tablets.
e. Denominator includes those subjects who were viremic at last time point on tenofovir disoproxil fumarate tablets monotherapy and had evaluable paired genotypic data.
f. Of the 18 subjects with treatment-emergent amino acid substitutions during Studies 0102 and 0103, 5 subjects had substitutions at conserved sites and 13 subjects had substitutions only at polymorphic sites, and 8 subjects had only transient substitutions that were not detected at the last time point on tenofovir disoproxil fumarate tablets.
g. Of the 11 HEPSERA-experienced subjects with treatment-emergent amino acid substitutions, 2 subjects had substitutions at conserved sites and 9 had substitutions only at polymorphic sites.
h. Of the 6 lamivudine-resistant subjects with treatment-emergent substitutions during Study 0121, 3 subjects had substitutions at conserved sites and 3 had substitutions only at polymorphic sites
Cross Resistance
Cross resistance has been observed between HBV nucleoside/nucleotide analogue reverse transcriptase inhibitors.
In cell based assays, HBV strains expressing the rtV173L, rtL180M, and rtM204I/V substitutions associated with resistance to lamivudine and telbivudine showed a susceptibility to tenofovir ranging from 0.7- to 3.4-fold that of wild type virus. The rtL180M and rtM204I/V double substitutions conferred 3.4-fold reduced susceptibility to tenofovir.
HBV strains expressing the rtL180M, rtT184G, rtS202G/I, rtM204V, and rtM250V substitutions associated with resistance to entecavir showed a susceptibility to tenofovir ranging from 0.6- to 6.9-fold that of wild type virus.
HBV strains expressing the adefovir resistance-associated substitutions rtA181V and/or rtN236T showed reductions in susceptibility to tenofovir ranging from 2.9- to 10-fold that of wild type virus. Strains containing the rtA181T substitution showed changes in susceptibility to tenofovir ranging from 0.9- to 1.5-fold that of wild type virus.
One hundred fifty-two subjects initiating tenofovir disoproxil fumarate tablets therapy in Studies 0102, 0103, 0106, 0108, and 0121 harbored HBV with known resistance substitutions to HBV nucleos(t)ide analogue reverse transcriptase inhibitors: 14 with adefovir resistance-associated substitutions (rtA181S/T/V and/or rtN236T), 135 with lamivudine resistance-associated substitutions (rtM204I/V), and 3 with both adefovir and lamivudine resistance-associated substitutions. Following up to 384 weeks of tenofovir disoproxil fumarate tablets treatment, 10 of the 14 subjects with adefovir-resistant HBV, 124 of the 135 subjects with lamivudine-resistant HBV, and 2 of the 3 subjects with both adefovir- and lamivudine-resistant HBV achieved and maintained virologic suppression (HBV DNA less than 400 copies/mL [69 IU/mL]). Three of the 5 subjects whose virus harbored both the rtA181T/V and rtN236T substitutions remained viremic.

13 NONCLINICAL TOXICOLOGY

13.1 Carcinogenesis & Mutagenesis & Impairment Of Fertility

Carcinogenesis
Long-term oral carcinogenicity studies of tenofovir DF in mice and rats were carried out at exposures up to approximately 16 times (mice) and 5 times (rats) those observed in humans at the therapeutic dose for HIV-1 infection. At the high dose in female mice, liver adenomas were increased at exposures 16 times that in humans. In rats, the study was negative for carcinogenic findings at exposures up to 5 times that observed in humans at the therapeutic dose.
Mutagenesis
Tenofovir DF was mutagenic in the in vitro mouse lymphoma assay and negative in an in vitro bacterial mutagenicity test (Ames test). In an in vivo mouse micronucleus assay, tenofovir DF was negative when administered to male mice.
Impairment of Fertility
There were no effects on fertility, mating performance or early embryonic development when tenofovir DF was administered to male rats at a dose equivalent to 10 times the human dose based on body surface area comparisons for 28 days prior to mating and to female rats for 15 days prior to mating through day seven of gestation. There was, however, an alteration of the estrous cycle in female rats.

13.2 Animal Pharmacology & OR Toxicology

Tenofovir and tenofovir DF administered in toxicology studies to rats, dogs, and monkeys at exposures (based on AUCs) greater than or equal to 6 fold those observed in humans caused bone toxicity. In monkeys the bone toxicity was diagnosed as osteomalacia. Osteomalacia observed in monkeys appeared to be reversible upon dose reduction or discontinuation of tenofovir. In rats and dogs, the bone toxicity manifested as reduced bone mineral density. The mechanism(s) underlying bone toxicity is unknown.
Evidence of renal toxicity was noted in 4 animal species. Increases in serum creatinine, BUN, glycosuria, proteinuria, phosphaturia, and/or calciuria and decreases in serum phosphate were observed to varying degrees in these animals. These toxicities were noted at exposures (based on AUCs) 2 to 20 times higher than those observed in humans. The relationship of the renal abnormalities, particularly the phosphaturia, to the bone toxicity is not known.

14 CLINICAL STUDIES

14.1 Clinical Efficacy in Adults with HIV-1 Infection

Treatment-Naïve Adult Patients
Study 903
Data through 144 weeks are reported for Study 903, a double-blind, active-controlled multicenter trial comparing tenofovir disoproxil fumarate tablets (300 mg once daily) administered in combination with lamivudine and efavirenz versus stavudine (d4T), lamivudine, and efavirenz in 600 antiretroviral-naïve subjects. Subjects had a mean age of 36 years (range 18 to 64); 74% were male, 64% were Caucasian, and 20% were Black. The mean baseline CD4^+ cell count was 279 cells/mm^3 (range 3 to 956) and median baseline plasma HIV-1 RNA was 77,600 copies/mL (range 417 to 5,130,000). Subjects were stratified by baseline HIV-1 RNA and CD4^+ cell count. Forty-three percent of subjects had baseline viral loads >100,000 copies/mL and 39% had CD4^+ cell counts <200 cells/mm^3. Treatment outcomes through 48 and 144 weeks are presented in Table 18.
Table 18 Outcomes of Randomized Treatment at Week 48 and 144 (Study 903)

Outcomes | At Week 48 |  | At Week 144
Outcomes | Tenofovir disoproxil fumarate Tablets+ 3TC+EFV (N=299) | d4T+ 3TC+EFV (N=301) | Tenofovir disoproxil fumarate Tablets+ 3TC+EFV (N=299) | d4T+3TC +EFV (N=301)
Respondera | 79% | 82% | 68% | 62%
Virologic failureb | 6% | 4% | 10% | 8%
Rebound | 5% | 3% | 8% | 7%
Never suppressed | 0% | 1% | 0% | 0%
Added an antiretroviral agent | 1% | 1% | 2% | 1%
Death | <1% | 1% | <1% | 2%
Discontinued due to adverse event | 6% | 6% | 8% | 13%
Discontinued for other reasonsc | 8% | 7% | 14% | 15%

a. Subjects achieved and maintained confirmed HIV-1 RNA <400 copies/mL through Week 48 and 144.
b. Includes confirmed viral rebound and failure to achieve confirmed <400 copies/mL through Week 48 and 144.
c. Includes lost to follow-up, subject’s withdrawal, noncompliance, protocol violation and other reasons.
Achievement of plasma HIV-1 RNA concentrations of less than 400 copies/mL at Week 144 was similar between the two treatment groups for the population stratified at baseline on the basis of HIV-1 RNA concentration (> or ≤100,000 copies/mL) and CD4^+ cell count (< or ≥200 cells/mm^3). Through 144 weeks of therapy, 62% and 58% of subjects in the tenofovir disoproxil fumarate tablets and stavudine arms, respectively, achieved and maintained confirmed HIV-1 RNA <50 copies/mL. The mean increase from baseline in CD4^+ cell count was 263 cells/mm3 for the tenofovir disoproxil fumarate tablets arm and 283 cells/mm3 for the stavudine arm.
Through 144 weeks, 11 subjects in the tenofovir disoproxil fumarate tablets group and 9 subjects in the stavudine group experienced a new CDC Class C event.
Study 934
Data through 144 weeks are reported for Study 934, a randomized, open-label, active-controlled multicenter trial comparing emtricitabine + tenofovir disoproxil fumarate tablets administered in combination with efavirenz versus zidovudine/lamivudine fixed-dose combination administered in combination with efavirenz in 511 antiretroviral-naïve subjects. From Weeks 96 to 144 of the trial, subjects received a fixed-dose combination of emtricitabine and tenofovir DF with efavirenz in place of emtricitabine + tenofovir disoproxil fumarate tablets with efavirenz. Subjects had a mean age of 38 years (range 18 to 80); 86% were male, 59% were Caucasian, and 23% were Black. The mean baseline CD4+ cell count was 245 cells/mm^3 (range 2 to 1191) and median baseline plasma HIV-1 RNA was 5.01 log10 copies/mL (range 3.56 to 6.54). Subjects were stratified by baseline CD4^+ cell count (< or ≥200 cells/mm^3); 41% had CD4^+ cell counts <200 cells/mm^3 and 51% of subjects had baseline viral loads >100,000 copies/mL. Treatment outcomes through 48 and 144 weeks for those subjects who did not have efavirenz resistance at baseline are presented in Table 19. Table 19 Outcomes of Randomized Treatment at Week 48 and 144 (Study 934)

Outcomes | At Week 48 |  | At Week 144
Outcomes | FTC + Tenofovir disoproxil fumarate Tablets+ EFV (N=244) | AZT/3TC +EFV (N=243) | FTC+Tenofovir disoproxil fumarate Tablets+EFV (N=227)a | AZT/3TC +EFV (N=229)a
Responderb | 84% | 73% | 71% | 58%
Virologic failurec | 2% | 4% | 3% | 6%
Rebound | 1% | 3% | 2% | 5%
Never suppressed | 0% | 0% | 0% | 0%
Change in antiretroviral regimen | 1% | 1% | 1% | 1%
Death | <1% | 1% | 1% | 1%
Discontinued due to adverse event | 4% | 9% | 5% | 12%
Discontinued for other reasonsd | 10% | 14% | 20% | 22%

a. Subjects who were responders at Week 48 or Week 96 (HIV-1 RNA <400 copies/mL) but did not consent to continue the trial after Week 48 or Week 96 were excluded from analysis.
b. Subjects achieved and maintained confirmed HIV-1 RNA <400 copies/mL through Weeks 48 and 144.
c. Includes confirmed viral rebound and failure to achieve confirmed <400 copies/mL through Weeks 48 and 144.
d. Includes lost to follow-up, subject withdrawal, noncompliance, protocol violation and other reasons.
Through Week 48, 84% and 73% of subjects in the emtricitabine + tenofovir disoproxil fumarate tablets group and the zidovudine/lamivudine group, respectively, achieved and maintained HIV-1 RNA <400 copies/mL (71% and 58% through Week 144). The difference in the proportion of subjects who achieved and maintained HIV-1 RNA <400 copies/mL through 48 weeks largely results from the higher number of discontinuations due to adverse events and other reasons in the zidovudine/lamivudine group in this open-label trial. In addition, 80% and 70% of subjects in the emtricitabine + tenofovir disoproxil fumarate tablets group and the zidovudine/lamivudine group, respectively, achieved and maintained HIV-1 RNA <50 copies/mL through Week 48 (64% and 56% through Week 144). The mean increase from baseline in CD4^+ cell count was 190 cells/mm^3 in the EMTRIVA + tenofovir disoproxil fumarate tablets group and 158 cells/mm^3 in the zidovudine/lamivudine group at Week 48 (312 and 271 cells/mm^3 at Week 144).
Through 48 weeks, 7 subjects in the emtricitabine + tenofovir disoproxil fumarate tablets group and 5 subjects in the zidovudine/lamivudine group experienced a new CDC Class C event (10 and 6 subjects through 144 weeks).
Treatment-Experienced Adult Patients
Study 907
Study 907 was a 24-week, double-blind, placebo-controlled multicenter trial of tenofovir disoproxil fumarate tablets added to a stable background regimen of antiretroviral agents in 550 treatment-experienced subjects. After 24 weeks of blinded trial treatment, all subjects continuing on trial were offered open-label tenofovir disoproxil fumarate tablets for an additional 24 weeks. Subjects had a mean baseline CD4+ cell count of 427 cells/mm3 (range 23 to 1385), median baseline plasma HIV-1 RNA of 2340 (range 50 to 75,000) copies/mL, and mean duration of prior HIV-1 treatment was 5.4 years. Mean age of the subjects was 42 years; 85% were male, 69% Caucasian, 17% Black, and 12% Hispanic.
The percent of subjects with HIV-1 RNA <400 copies/mL and outcomes of subjects through 48 weeks are summarized in Table 20.
Table 20 Outcomes of Randomized Treatment (Study 907)

Outcomes | 0–24 weeks |  | 0–48 weeks | 24–48 weeks
Outcomes | Tenofovir disoproxil fumarate Tablets (N=368) | Placebo (N=182) | Tenofovir disoproxil fumarate Tablets (N=368) | Placebo Crossover to Tenofovir disoproxil fumarate Tablets (N=170)
HIV-1 RNA <400 copies/mLa | 40% | 11% | 28% | 30%
Virologic failureb | 53% | 84% | 61% | 64%
Discontinued due to adverse event | 3% | 3% | 5% | 5%
Discontinued for other reasonsc | 3% | 3% | 5% | 1%

a. Subjects with HIV-1 RNA <400 copies/mL and no prior study drug discontinuation at Week 24 and 48, respectively.
b. Subjects with HIV-1 RNA ≥400 copies/mL efficacy failure or missing HIV-1 RNA at Week 24 and 48, respectively.
c. Includes lost to follow-up, subject withdrawal, noncompliance, protocol violation, and other reasons.
At 24 weeks of therapy, there was a higher proportion of subjects in the tenofovir disoproxil fumarate tablets arm compared to the placebo arm with HIV-1 RNA <50 copies/mL (19% and 1%, respectively). Mean change in absolute CD4^+ cell counts by Week 24 was +11 cells/mm3 for the tenofovir disoproxil fumarate tablets group and -5 cells/mm^3 for the placebo group. Mean change in absolute CD4^+ cell counts by Week 48 was +4 cells/mm^3 for the tenofovir disoproxil fumarate tablets group.
Through Week 24, one subject in the tenofovir disoproxil fumarate tablets group and no subjects in the placebo arm experienced a new CDC Class C event.

14.2 Clinical Efficacy in Adults with Chronic Hepatitis B

HBeAg-Negative Chronic Hepatitis B
Study 0102 was a Phase 3, randomized, double-blind, active-controlled trial of tenofovir disoproxil fumarate tablets 300 mg compared to HEPSERA 10 mg in 375 HBeAg- (anti-HBe^+) subjects with compensated liver function, the majority of whom were nucleoside-naïve. The mean age of subjects was 44 years; 77% were male, 25% were Asian, 65% were Caucasian, 17% had previously received alpha-interferon therapy, and 18% were nucleoside-experienced (16% had prior lamivudine experience). At baseline, subjects had a mean Knodell necroinflammatory score of 7.8; mean plasma HBV DNA was 6.9 log10 copies/mL; and mean serum ALT was 140 U/L.
HBeAg-Positive Chronic Hepatitis B
Study 0103 was a Phase 3, randomized, double-blind, active-controlled trial of tenofovir disoproxil fumarate tablets 300 mg compared to HEPSERA 10 mg in 266 HBeAg+ nucleoside-naïve subjects with compensated liver function. The mean age of subjects was 34 years; 69% were male, 36% were Asian, 52% were Caucasian, 16% had previously received alpha-interferon therapy, and <5% were nucleoside experienced. At baseline, subjects had a mean Knodell necroinflammatory score of 8.4; mean plasma HBV DNA was 8.7 log10 copies /mL; and mean serum ALT was 147 U/L.
The primary data analysis was conducted after all subjects reached 48 weeks of treatment and results are summarized below.
The primary efficacy endpoint in both trials was complete response to treatment defined as HBV DNA <400 copies/mL (69 IU/mL) and Knodell necroinflammatory score improvement of at least 2 points, without worsening in Knodell fibrosis at Week 48 (Table 21).
Table 21 Histological, Virological, Biochemical, and Serological Response at Week 48

 | 0102 (HBeAg-) |  | 0103 (HBeAg+)
 | Tenofovir disoproxil fumarate Tablets (N=250) | HEPSERA (N=125) | Tenofovir disoproxil fumarate Tablets (N=176) | HEPSERA (N=90)
Complete Response | 71% | 49% | 67% | 12%
Histology Histological Responsea | 72% | 69% | 74% | 68%
HBV DNA <400 copies/mL (<69 IU/mL) | 93% | 63% | 76% | 13%
ALT Normalized ALTb | 76% | 77% | 68% | 54%
Serology HBeAg Loss/ Seroconversion | NAc | NAc | 20%/19% | 16%/16%
HBsAg Loss/ Seroconversion | 0/0 | 0/0 | 3%/1% | 0/0

a. Knodell necroinflammatory score improvement of at least 2 points without worsening in Knodell fibrosis.
b. The population used for analysis of ALT normalization included only subjects with ALT above ULN at baseline.
c. NA = Not Applicable
Treatment Beyond 48 Weeks
In Studies 0102 (HBeAg-negative) and 0103 (HBeAg-positive), subjects who completed double-blind treatment (389 and 196 subjects who were originally randomized to tenofovir disoproxil fumarate tablets and HEPSERA, respectively) were eligible to roll over to open-label tenofovir disoproxil fumarate tablets with no interruption in treatment.
In Study 0102, 266 of 347 subjects who entered the open-label period (77%) continued in the study through Week 384. Among subjects randomized to tenofovir disoproxil fumarate tablets followed by open-label treatment with tenofovir disoproxil fumarate tablets, 73% had HBV DNA <400 copies/mL (69 IU/mL), and 63% had ALT normalization at Week 384. Among subjects randomized to HEPSERA followed by open-label treatment with tenofovir disoproxil fumarate tablets, 80% had HBV DNA <400 copies/mL (69 IU/mL) and 70% had ALT normalization through Week 384. At Week 384, both HBsAg loss and seroconversion were approximately 1% in both treatment groups.
In Study 0103, 146 of 238 subjects who entered the open-label period (61%) continued in the study through Week 384. Among subjects randomized to tenofovir disoproxil fumarate tablets, 49% had HBV DNA <400 copies/mL (69 IU/mL), 42% had ALT normalization, and 20% had HBeAg loss (13% seroconversion to anti-HBe antibody) through Week 384. Among subjects randomized to HEPSERA followed by open-label treatment with tenofovir disoproxil fumarate tablets, 56% had HBV DNA <400 copies/mL (69 IU/mL), 50% had ALT normalization, and 28% had HBeAg loss (19% seroconversion to anti-HBe antibody) through Week 384. At Week 384, HBsAg loss and seroconversion were 11% and 8%, respectively, in subjects initially randomized to tenofovir disoproxil fumarate tablets and 12% and 10%, respectively, in subjects initially randomized to HEPSERA.
Of the originally randomized and treated 641 subjects in the two studies, liver biopsy data from 328 subjects who received continuing open-label treatment with tenofovir disoproxil fumarate tablets monotherapy were available for analysis at baseline, Week 48, and Week 240. There were no apparent differences between the subset of subjects who had liver biopsy data at Week 240 and those subjects remaining on open-label tenofovir disoproxil fumarate tablets without biopsy data that would be expected to affect histological outcomes at Week 240. Among the 328 subjects evaluated, the observed histological response rates were 80% and 88% at Week 48 and Week 240, respectively. In the subjects without cirrhosis at baseline (Ishak fibrosis score 0 to 4), 92% (216/235) and 95% (223/235) had either improvement or no change in Ishak fibrosis score at Week 48 and Week 240, respectively. In subjects with cirrhosis at baseline (Ishak fibrosis score 5 to 6), 97% (90/93) and 99% (92/93) had either improvement or no change in Ishak fibrosis score at Week 48 and Week 240, respectively. Twenty-nine percent (27/93) and 72% (67/93) of subjects with cirrhosis at baseline experienced regression of cirrhosis by Week 48 and Week 240, respectively, with a reduction in Ishak fibrosis score of at least 2 points. No definitive conclusions can be established about the remaining study population who were not part of this subset analysis.
Patients with Lamivudine-Resistant Chronic Hepatitis B
Study 121 was a randomized, double-blind, active-controlled trial evaluating the safety and efficacy of tenofovir disoproxil fumarate tablets compared to an unapproved antiviral regimen in subjects with chronic hepatitis B, persistent viremia (HBV DNA ≥1,000 IU/mL), and genotypic evidence of lamivudine resistance (rtM204I/V +/- rtL 180M). One hundred forty-one adult subjects were randomized to the tenofovir disoproxil fumarate tablets treatment arm. The mean age of subjects randomized to tenofovir disoproxil fumarate tablets was 47 years (range 18 to 73); 74% were male, 59% were Caucasian, and 37% were Asian. At baseline, 54% of subjects were HBeAg-negative, 46% were HBeAg-positive, and 56% had abnormal ALT. Subjects had a mean HBV DNA of 6.4 log10 copies/mL and mean serum ALT of 71 U/L at baseline.
After 96 weeks of treatment, 126 of 141 subjects (89%) randomized to tenofovir disoproxil fumarate tablets had HBV DNA <400 copies/mL (69 IU/mL), and 49 of 79 subjects (62%) with abnormal ALT at baseline had ALT normalization. Among the HBeAg-positive subjects randomized to tenofovir disoproxil fumarate tablets, 10 of 65 subjects (15%) experienced HBeAg loss and 7 of 65 subjects (11%) experienced anti-HBe seroconversion through Week 96. The proportion of subjects with HBV DNA concentrations below 400 copies/mL (69 IU/mL) at Week 96 was similar between the tenofovir disoproxil fumarate tablets monotherapy and the comparator arms.
Across the combined chronic hepatitis B treatment trials, the number of subjects with adefovir-resistance associated substitutions at baseline was too small to establish efficacy in this subgroup.
Patients with Chronic Hepatitis B and Decompensated Liver Disease
Tenofovir disoproxil fumarate tablets were studied in a small randomized, double-blind, active-controlled trial evaluating the safety of tenofovir disoproxil fumarate tablets compared to other antiviral drugs in subjects with chronic hepatitis B and decompensated liver disease through 48 weeks (Study 0108).
Forty-five adult subjects (37 males and 8 females) were randomized to the tenofovir disoproxil fumarate tablets treatment arm. At baseline, 69% subjects were HBeAg-negative and 31% were HBeAg-positive. Subjects had a mean Child-Pugh score of 7, a mean MELD score of 12, mean HBV DNA of 5.8 log10 copies/mL, and mean serum ALT of 61 U/L at baseline. Trial endpoints were discontinuation due to an adverse event and confirmed increase in serum creatinine ≥ 0.5 mg/dL or confirmed serum phosphorus of < 2 mg/dL [See Adverse Reactions (6.1)].
At 48 weeks, 31/44 (70%) and 12/26 (46%) tenofovir disoproxil fumarate-treated subjects achieved an HBV DNA <400 copies/mL (69 IU/mL), and normalized ALT, respectively. The trial was not designed to evaluate treatment impact on clinical endpoints such as progression of liver disease, need for liver transplantation, or death.

16 HOW SUPPLIED/STORAGE AND HANDLING

Tablets
Tenofovir disoproxil fumarate tablets, 300 mg, are white colored, almond shaped, film coated tablets contain 300 mg of tenofovir DF, which is equivalent to 245 mg of tenofovir disoproxil, are debossed with ‘H’ on one side and ‘123’ on other side. They are packaged as follows:
Bottle of 30 tablets (NDC 42291-800-30)

Store at 20° to 25°C (68° to 77°F) [see USP Controlled Room Temperature].
Keep the bottle tightly closed. Do not use if seal over bottle opening is broken or missing.

17 PATIENT COUNSELING INFORMATION

Advise the patient to read the FDA-approved patient labeling (Patient Information).
Inform patients that tenofovir disoproxil fumarate tablets are not a cure for HIV-1 infection and patients may continue to experience illnesses associated with HIV-1 infection, including opportunistic infections. Patients should remain under the care of a physician when using tenofovir disoproxil fumarate tablets.
Advise patients to avoid doing things that can spread HIV or HBV to others.
• Do not share needles or other injection equipment.
• Do not share personal items that can have blood or body fluids on them, like toothbrushes and razor blades.
• Do not have any kind of sex without protection. Always practice safer sex by using a latex or polyurethane condom to lower the chance of sexual contact with semen, vaginal secretions, or blood.
• Do not breastfeed. Tenofovir is excreted in breast milk and it is not known whether it can harm the baby. Mothers with HIV-1 should not breastfeed because HIV-1 can be passed to the baby in the breast milk.
Inform patients that:
• The long-term effects of tenofovir disoproxil fumarate tablets are unknown.
• Tenofovir disoproxil fumarate tablets are for oral ingestion only.
• Tenofovir disoproxil fumarate tablets should not be discontinued without first informing their physician.
• If you have HIV-1 infection, with or without HBV coinfection, it is important to take tenofovir disoproxil fumarate tablets with combination therapy.
• It is important to take tenofovir disoproxil fumarate tablets on a regular dosing schedule and to avoid missing doses.
• Severe acute exacerbations of hepatitis have been reported in patients who are infected with HBV or coinfected with HBV and HIV-1 and have discontinued tenofovir disoproxil fumarate tablets [See Warnings and Precautions (5.1)].
• Renal impairment, including cases of acute renal failure and Fanconi syndrome, has been reported. Tenofovir disoproxil fumarate tablets should be avoided with concurrent or recent use of a nephrotoxic agent (e.g., high-dose or multiple NSAIDs) [See Warnings and Precautions (5.2)].
• Lactic acidosis and severe hepatomegaly with steatosis, including fatal cases, have been reported. Treatment with tenofovir disoproxil fumarate tablets should be suspended in any patient who develops clinical symptoms suggestive of lactic acidosis or pronounced hepatotoxicity [See Warnings and Precautions (5.3)].
• Tenofovir disoproxil fumarate tablets should not be coadministered with ATRIPLA, BIKTARVY, COMPLERA, DESCOVY, GENVOYA, ODEFSEY, STRIBILD, TRUVADA, or VEMLIDY [See Warnings and Precautions (5.4)].
• Tenofovir disoproxil fumarate tablets should not be administered in combination with HEPSERA [See Warnings and Precautions (5.4)].
• Decreases in bone mineral density have been observed with the use of tenofovir disoproxil fumarate tablets. Bone mineral density monitoring should be considered in patients who have a history of pathologic bone fracture or at risk for osteopenia [See Warnings and Precautions (5.6)].
• In some patients treated with combination antiretroviral therapy, including tenofovir disoproxil fumarate tablets, signs and symptoms of inflammation from previous infections may occur soon after anti-HIV treatment is started. It is believed that these symptoms are due to an improvement in the body’s immune response, enabling the body to fight infections that may have been present with no obvious symptoms. Advise patients to inform their healthcare provider immediately of any symptoms of infection [See Warnings and Precautions (5.7)].
• In the treatment of chronic hepatitis B, the optimal duration of treatment is unknown. The relationship between response and long-term prevention of outcomes such as hepatocellular carcinoma is not known.
All brand names listed are the registered trademarks of their respective owners and are not trademarks of AvKARE.

Manufactured for:
AvKARE
Pulaski, TN 38478

Mfg. Rev. 09/18
AV Rev. 04/2020 (P)

PATIENT INFORMATION

Tenofovir Disoproxil Fumarate Tablets
(ten OF oh vir dye soe PROX il FUE ma rate)
Read this Patient Information before you start taking tenofovir disoproxil fumarate tablets and each time you get a refill. There may be new information. This information does not take the place of talking with your healthcare provider about your medical condition or treatment.
What is the most important information I should know about tenofovir disoproxil fumarate tablets?
Tenofovir disoproxil fumarate tablets can cause serious side effects, including:
• Worsening of your Hepatitis B infection. Your hepatitis B virus (HBV) infection may become worse (flare-up) if you take tenofovir disoproxil fumarate tablets and then stop it. A “flare-up” is when your HBV infection suddenly returns in a worse way than before.
o Do not let your tenofovir disoproxil fumarate tablets run out. Refill your prescription or talk to your healthcare provider before your tenofovir disoproxil fumarate is all gone.
o Do not stop taking tenofovir disoproxil fumarate tablets without first talking to your healthcare provider.
o If you stop taking tenofovir disoproxil fumarate tablets, your healthcare provider will need to check your health often and do blood tests regularly to check your HBV infection. Tell your healthcare provider about any new or unusual symptoms you may have after you stop taking tenofovir disoproxil fumarate tablets.
Talk to your doctor about taking an HIV test before starting treatment with tenofovir disoproxil fumarate tablets for chronic hepatitis B. You should also get a test for HBV if you are taking tenofovir disoproxil fumarate tablets for treatment of HIV.
What are tenofovir disoproxil fumarate tablets?
Tenofovir disoproxil fumarate tablet is a prescription medicine used:
• with other antiviral medicines to treat Human Immunodeficiency Virus-1 (HIV-1) in people 2 years of age and older.
o When used with other HIV medicines, tenofovir disoproxil fumarate tablets may reduce the amount of HIV in your blood (called “viral load”). Tenofovir disoproxil fumarate tablets may also help to increase the number of CD4 (T) cells in your blood which help fight off other infections. Reducing the amount of HIV and increasing the CD4 (T) cell count may improve your immune system. This may reduce your risk of death or infections that can happen when your immune system is weak (opportunistic infections).
o Tenofovir disoproxil fumarate tablets does not cure HIV infection or AIDS. People taking tenofovir disoproxil fumarate tablets may still develop infections or other conditions associated with HIV infection.
o You must stay on continuous HIV therapy to control infection and decrease HIV-related illnesses.
o It is very important that you stay under the care of your healthcare provider.
o HIV is the virus that causes AIDS (Acquired Immune Deficiency Syndrome).
o It is not known if tenofovir disoproxil fumarate tablets are safe and effective for the treatment of HIV-1 infection in children under the age of 2 years.
• to treat chronic (long-lasting) hepatitis B virus (HBV) in people 12 years of age and older.
o Tenofovir disoproxil fumarate tablets may lower the amount of HBV in your body.
o Tenofovir disoproxil fumarate tablets may improve the condition of your liver.
o It is not known if tenofovir disoproxil fumarate tablets are safe and effective for treatment of chronic hepatitis B in children under the age of 12 years.
What should I tell my healthcare provider before taking tenofovir disoproxil fumarate tablets?
Before you take tenofovir disoproxil fumarate tablets, tell your healthcare provider if you:
• have liver problems, including hepatitis B (HBV) infection.
• have kidney problems.
• have bone problems.
• have any other medical conditions, including HIV infection.
• are pregnant or plan to become pregnant. It is not known if tenofovir disoproxil fumarate tablets will harm your unborn baby.
Pregnancy Registry. There is a pregnancy registry for women who take antiviral medicines during pregnancy. Its purpose is to collect information about the health of you and your baby. Talk to your healthcare provider about how you can take part in this registry.
• are breastfeeding or plan to breastfeed. Do not breastfeed if you are taking tenofovir disoproxil fumarate tablets. Tenofovir passes into your breast milk. You should not breastfeed because of the risk of passing HIV to your baby. Talk to your healthcare provider about the best way to feed your baby.
Tell your healthcare provider about all the medicines you take, including prescription and non-prescription medicines, vitamins, and herbal supplements.
Some medicines may affect how tenofovir disoproxil fumarate tablets work.
• Keep a list of your medicines and show it to your healthcare provider and pharmacist when you get a new medicine. You can ask your healthcare provider or pharmacist for a list of medicines that interact with tenofovir disoproxil fumarate tablets.
• Do not start a new medicine without telling your healthcare provider. Your healthcare provider can tell you if it is safe to take tenofovir disoproxil fumarate tablets with other medicines.
How should I take tenofovir disoproxil fumarate tablets?
• See "What is the most important information I should know about tenofovir disoproxil fumarate tablets?"
• Take tenofovir disoproxil fumarate tablets exactly as your healthcare provider tells you to take them.
• Take tenofovir disoproxil fumarate tablets at the same time every day.
• For adults and children 12 years of age and older, the usual dose of tenofovir disoproxil fumarate tablets is one 300 mg tablet each day.
• If you are an adult with kidney problems, your healthcare provider may tell you to take tenofovir disoproxil fumarate tablets less often.
• For children 2 to 12 years of age, your healthcare provider will prescribe the right dose of tenofovir disoproxil fumarate tablets based on your child’s body weight.
• Tell your healthcare provider if your child has problems with swallowing tablets.
• Take tenofovir disoproxil fumarate tablets by mouth, with or without food.
• Do not miss a dose of tenofovir disoproxil fumarate tablets. If you miss a dose of tenofovir disoproxil fumarate tablets, take the missed dose as soon as you remember. If it is almost time for your next dose of tenofovir disoproxil fumarate tablets, do not take the missed dose. Take the next dose of tenofovir disoproxil fumarate tablets at your regular time.
• If you take too much tenofovir disoproxil fumarate, call your local poison control center or go right away to the nearest hospital emergency room.
What are the possible side effects of tenofovir disoproxil fumarate tablets?
Tenofovir disoproxil fumarate tablets may cause serious side effects, including:
• See "What is the most important information I should know about tenofovir disoproxil fumarate tablets"?
• New or worse kidney problems, including kidney failure, can happen in some people who take tenofovir disoproxil fumarate tablets. Your healthcare provider should do blood tests to check your kidneys before you start treatment with tenofovir disoproxil fumarate tablets. If you have had kidney problems in the past or need to take another medicine that can cause kidney problems, your healthcare provider may need to do blood tests to check your kidneys during your treatment with tenofovir disoproxil fumarate tablets.
• Too much lactic acid in your blood (lactic acidosis). Too much lactic acid is a serious but rare medical emergency that can lead to death. Tell your healthcare provider right away if you get these symptoms: weakness or being more tired than usual, unusual muscle pain, being short of breath or fast breathing, stomach pain with nausea and vomiting, cold or blue hands and feet, feel dizzy or lightheaded, or a fast or abnormal heartbeat.
• Severe liver problems. In rare cases, severe liver problems can happen that can lead to death. Tell your healthcare provider right away if you get these symptoms: skin or the white part of your eyes turns yellow, dark “tea-colored” urine, light-colored stools, loss of appetite for several days or longer, nausea, or stomach-area pain.
• Bone problems can happen in some people who take tenofovir disoproxil fumarate tablets. Bone problems include bone pain, softening or thinning (which may lead to fractures). Your healthcare provider may need to do additional tests to check your bones.
• Changes in your immune system (Immune Reconstitution Syndrome) can happen when you start taking HIV medicines. Your immune system may get stronger and begin to fight infections that have been hidden in your body for a long time. Tell your healthcare provider if you start having new symptoms after starting your HIV medicine.
The most common side effects in all people who take tenofovir disoproxil fumarate tablets are:
• nausea • pain
• rash • depression
• diarrhea • weakness
• headache
In some people with advanced HBV-infection, other common side effects may include:
• sleeping problems
• itching
• vomiting
• dizziness
• fever
Tell your healthcare provider if you have any side effect that bothers you or that does not go away.
These are not all the possible side effects of tenofovir disoproxil fumarate tablets. For more information, ask your healthcare provider or pharmacist.
Call your doctor for medical advice about side effects. You may report side effects to FDA at 1-800-FDA-1088.
How should I store tenofovir disoproxil fumarate tablets?
• Store tenofovir disoproxil fumarate tablets at 20° to 25°C (68° to 77°F) [see USP Controlled Room Temperature].
• Do not use tenofovir disoproxil fumarate tablets if the seal over the bottle opening is broken or missing.
• Keep the bottle tightly closed.
Keep tenofovir disoproxil fumarate tablets and all medicines out of the reach of children.
General information about tenofovir disoproxil fumarate tablets:
Medicines are sometimes prescribed for purposes other than those listed in a Patient Information leaflet. Do not use tenofovir disoproxil fumarate tablets for a condition for which it was not prescribed. Do not give tenofovir disoproxil fumarate tablets to other people, even if they have the same condition you have. It may harm them.
Avoid doing things that can spread HIV-1 or HBV infection to others.
• Do not share or re-use needles or other injection equipment.
• Do not share personal items that can have blood or body fluids on them, like toothbrushes and razor blades.
• Do not have any kind of sex without protection. Always practice safe sex by using a latex or polyurethane condom to lower the chance of sexual contact with semen, vaginal secretions, or blood.
A vaccine is available to protect people at risk for becoming infected with HBV. You can ask your healthcare provider for information about this vaccine.
This leaflet summarizes the most important information about tenofovir disoproxil fumarate tablets. If you would like more information, talk with your healthcare provider. You can ask your pharmacist or healthcare provider for information about tenofovir disoproxil fumarate tablets that is written for health professionals.
For more Information call AvKARE at 1-855-361-3993.
What are the ingredients in tenofovir disoproxil fumarate tablets?
Active Ingredient: tenofovir disoproxil fumarate
Inactive Ingredients:
Tenofovir disoproxil fumarate tablets: croscarmellose sodium, lactose monohydrate, magnesium stearate, microcrystalline cellulose and pregelatinized starch.
Tablet Coating:
The tablets are coated with opadry II white which contains hypromellose, lactose monohydrate, titanium dioxide and triacetin.
This Patient Information has been approved by the U.S. Food and Drug Administration.

Manufactured for:
AvKARE
Pulaski, TN 38478

Mfg. Rev. 09/18
AV Rev. 04/2020 (P)

All brand names listed are the registered trademarks of their respective owners and are not trademarks of AvKARE.